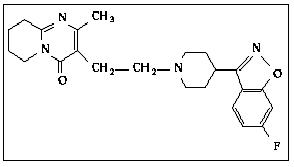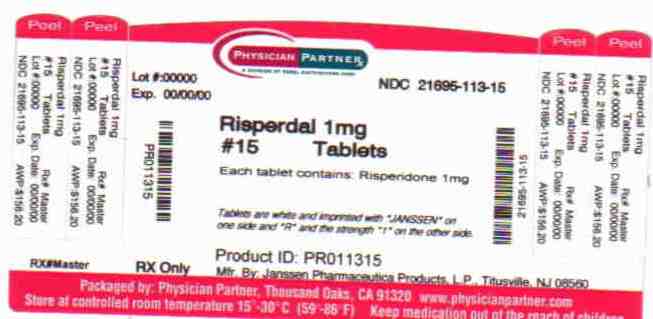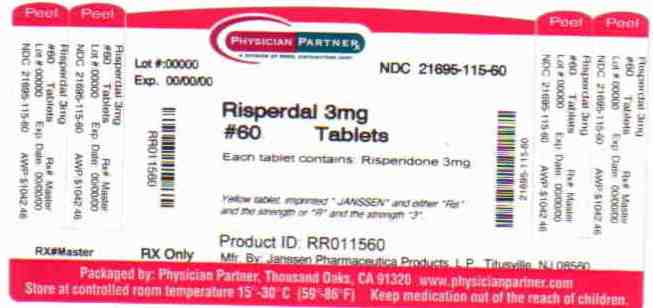 DRUG LABEL: RISPERDAL
NDC: 21695-113 | Form: TABLET
Manufacturer: Rebel Distributors Corp
Category: prescription | Type: HUMAN PRESCRIPTION DRUG LABEL
Date: 20101227

ACTIVE INGREDIENTS: risperidone 1 mg/1 1
INACTIVE INGREDIENTS: silicon dioxide; HYPROMELLOSES; anhydrous lactose; magnesium stearate; cellulose, microcrystalline; propylene glycol; sodium lauryl sulfate; starch, corn

HIGHLIGHTS OF PRESCRIBING INFORMATION

These highlights do not include all the information needed to use RISPERDAL® safely and effectively. See full prescribing information for RISPERDAL®.
RISPERDAL® (risperidone) tablets, RISPERDAL® (risperidone) oral solution, RISPERDAL® M-TAB® (risperidone) orally disintegrating tablets
Initial U.S. Approval: 1993

RECENT MAJOR CHANGES

Warnings and Precautions, Leukopenia, Neutropenia, and Agranulocytosis (5.8) | 07/2009

BOXED WARNING

WARNING: INCREASED MORTALITY IN ELDERLY PATIENTS WITH DEMENTIA-RELATED PSYCHOSIS

See full prescribing information for complete boxed warning.

Elderly patients with dementia-related psychosis treated with antipsychotic drugs are at an increased risk of death. RISPERDAL® is not approved for use in patients with dementia-related psychosis. (5.1)

1 INDICATIONS AND USAGE

RISPERDAL® is an atypical antipsychotic agent indicated for:

- Treatment of schizophrenia in adults and adolescents aged 13–17 years (1.1)
- Alone, or in combination with lithium or valproate, for the short-term treatment of acute manic or mixed episodes associated with Bipolar I Disorder in adults, and alone in children and adolescents aged 10–17 years (1.2)
- Treatment of irritability associated with autistic disorder in children and adolescents aged 5–16 years (1.3)

2 DOSAGE AND ADMINISTRATION

 | Initial Dose | Titration | Target Dose | Effective Dose Range
Schizophrenia- adults (2.1) | 2 mg/day | 1–2 mg daily | 4–8 mg daily | 4–16 mg/day
Schizophrenia – adolescents (2.1) | 0.5mg/day | 0.5– 1 mg daily | 3mg/day | 1–6 mg/day
Bipolar mania – adults (2.2) | 2–3 mg/day | 1mg daily | 1–6mg/day | 1–6 mg/day
Bipolar mania in children/adolescents (2.2) | 0.5 mg/day | 0.5–1mg daily | 2.5mg/day | 0.5–6 mg/day
Irritability associated with autistic disorder (2.3) | 0.25 mg/day (<20 kg) 0.5 mg/day (≥20 kg) | 0.25–0.5 mg at ≥ 2 weeks | 0.5 mg/day (<20 kg) 1 mg/day (≥20 kg) | 0.5–3 mg/day

3 DOSAGE FORMS AND STRENGTHS

- Tablets: 0.25 mg, 0.5 mg, 1 mg, 2 mg, 3 mg, and 4 mg (3)
- Oral solution: 1 mg/mL (3)
- Orally disintegrating tablets: 0.5 mg, 1 mg, 2 mg, 3 mg, and 4 mg (3)

4 CONTRAINDICATIONS

- Known hypersensitivity to the product (4)

5 WARNINGS AND PRECAUTIONS

- Cerebrovascular events, including stroke, in elderly patients with dementia-related psychosis. RISPERDAL® is not approved for use in patients with dementia-related psychosis (5.2)
- Neuroleptic Malignant Syndrome (5.3)
- Tardive dyskinesia (5.4)
- Hyperglycemia and diabetes mellitus (5.5)
- Hyperprolactinemia (5.6)
- Orthostatic hypotension (5.7)
- Leukopenia, Neutropenia, and Agranulocytosis: has been reported with antipsychotics, including risperidone. Patients with a history of a clinically significant low white blood cell count (WBC) or a drug-induced leukopenia/neutropenia should have their complete blood count (CBC) monitored frequently during the first few months of therapy and discontinuation of RISPERDAL® should be considered at the first sign of a clinically significant decline in WBC in the absence of other causative factors. (5.8)
- Potential for cognitive and motor impairment (5.9)
- Seizures (5.10)
- Dysphagia (5.11)
- Priapism (5.12)
- Thrombotic Thrombocytopenic Purpura (TTP) (5.13)
- Disruption of body temperature regulation (5.14)
- Antiemetic Effect (5.15)
- Suicide (5.16)
- Increased sensitivity in patients with Parkinson's disease or those with dementia with Lewy bodies (5.17)
- Diseases or conditions that could affect metabolism or hemodynamic responses (5.17)

6 ADVERSE REACTIONS

The most common adverse reactions in clinical trials (≥10%) were somnolence, appetite increased, fatigue, rhinitis, upper respiratory tract infection, vomiting, coughing, urinary incontinence, saliva increased, constipation, fever, Parkinsonism, dystonia, abdominal pain, anxiety, nausea, dizziness, dry mouth, tremor, rash, akathisia, and dyspepsia. (6)

The most common adverse reactions that were associated with discontinuation from clinical trials were somnolence, nausea, abdominal pain, dizziness, vomiting, agitation, and akathisia. (6)

To report SUSPECTED ADVERSE REACTIONS, contact Janssen, Division of Ortho-McNeil-Janssen Pharmaceuticals, Inc. at 1-800-JANSSEN (1-800-526-7736) or FDA at 1-800-FDA-1088 or www.fda.gov/medwatch

7 DRUG INTERACTIONS

- Due to CNS effects, use caution when administering with other centrally-acting drugs. Avoid alcohol. (7.1)
- Due to hypotensive effects, hypotensive effects of other drugs with this potential may be enhanced. (7.2)
- Effects of levodopa and dopamine agonists may be antagonized. (7.3)
- Cimetidine and ranitidine increase the bioavailability of risperidone. (7.5)
- Clozapine may decrease clearance of risperidone. (7.6)
- Fluoxetine and paroxetine increase plasma concentrations of risperidone. (7.10)
- Carbamazepine and other enzyme inducers decrease plasma concentrations of risperidone. (7.11)

8 USE IN SPECIFIC POPULATIONS

- Nursing Mothers: should not breast feed. (8.3)
- Pediatric Use: safety and effectiveness not established for schizophrenia less than 13 years of age, for bipolar mania less than 10 years of age, and for autistic disorder less than 5 years of age. (8.4)
- Elderly or debilitated; severe renal or hepatic impairment; predisposition to hypotension or for whom hypotension poses a risk: Lower initial dose (0.5 mg twice daily), followed by increases in dose in increments of no more than 0.5 mg twice daily. Increases to dosages above 1.5 mg twice daily should occur at intervals of at least 1 week. (8.5, 2.4)

FULL PRESCRIBING INFORMATION

BOXED WARNING

Elderly patients with dementia-related psychosis treated with antipsychotic drugs are at an increased risk of death. Analyses of 17 placebo-controlled trials (modal duration of 10 weeks), largely in patients taking atypical antipsychotic drugs, revealed a risk of death in drug-treated patients of between 1.6 to 1.7 times the risk of death in placebo-treated patients. Over the course of a typical 10-week controlled trial, the rate of death in drug-treated patients was about 4.5%, compared to a rate of about 2.6% in the placebo group. Although the causes of death were varied, most of the deaths appeared to be either cardiovascular (e.g., heart failure, sudden death) or infectious (e.g., pneumonia) in nature. Observational studies suggest that, similar to atypical antipsychotic drugs, treatment with conventional antipsychotic drugs may increase mortality. The extent to which the findings of increased mortality in observational studies may be attributed to the antipsychotic drug as opposed to some characteristic(s) of the patients is not clear. RISPERDAL® (risperidone) is not approved for the treatment of patients with dementia-related psychosis. [See Warnings and Precautions (5.1)]

1 INDICATIONS AND USAGE

1.1 Schizophrenia

Adults

RISPERDAL® (risperidone) is indicated for the acute and maintenance treatment of schizophrenia [see Clinical Studies (14.1)].

Adolescents

RISPERDAL® is indicated for the treatment of schizophrenia in adolescents aged 13–17 years [see Clinical Studies (14.1)].

1.2 Bipolar Mania

Monotherapy - Adults and Pediatrics

RISPERDAL® is indicated for the short-term treatment of acute manic or mixed episodes associated with Bipolar I Disorder in adults and in children and adolescents aged 10–17 years [see Clinical Studies (14.2)].

Combination Therapy – Adults

The combination of RISPERDAL® with lithium or valproate is indicated for the short-term treatment of acute manic or mixed episodes associated with Bipolar I Disorder [see Clinical Studies (14.3)].

1.3 Irritability Associated with Autistic Disorder

Pediatrics

RISPERDAL® is indicated for the treatment of irritability associated with autistic disorder in children and adolescents aged 5–16 years, including symptoms of aggression towards others, deliberate self-injuriousness, temper tantrums, and quickly changing moods [see Clinical Studies (14.4)].

2 DOSAGE AND ADMINISTRATION

2.1 Schizophrenia

Adults

Usual Initial Dose

RISPERDAL® can be administered once or twice daily. Initial dosing is generally 2 mg/day. Dose increases should then occur at intervals not less than 24 hours, in increments of 1–2 mg/day, as tolerated, to a recommended dose of 4–8 mg/day. In some patients, slower titration may be appropriate. Efficacy has been demonstrated in a range of 4–16 mg/day [see Clinical Studies (14.1)]. However, doses above 6 mg/day for twice daily dosing were not demonstrated to be more efficacious than lower doses, were associated with more extrapyramidal symptoms and other adverse effects, and are generally not recommended. In a single study supporting once-daily dosing, the efficacy results were generally stronger for 8 mg than for 4 mg. The safety of doses above 16 mg/day has not been evaluated in clinical trials.

Maintenance Therapy

While it is unknown how long a patient with schizophrenia should remain on RISPERDAL®, the effectiveness of RISPERDAL® 2 mg/day to 8 mg/day at delaying relapse was demonstrated in a controlled trial in patients who had been clinically stable for at least 4 weeks and were then followed for a period of 1 to 2 years [see Clinical Studies (14.1)]. Patients should be periodically reassessed to determine the need for maintenance treatment with an appropriate dose.

Adolescents

The dosage of RISPERDAL® should be initiated at 0.5 mg once daily, administered as a single-daily dose in either the morning or evening. Dosage adjustments, if indicated, should occur at intervals not less than 24 hours, in increments of 0.5 or 1 mg/day, as tolerated, to a recommended dose of 3 mg/day. Although efficacy has been demonstrated in studies of adolescent patients with schizophrenia at doses between 1 and 6 mg/day, no additional benefit was seen above 3 mg/day, and higher doses were associated with more adverse events. Doses higher than 6 mg/day have not been studied.

Patients experiencing persistent somnolence may benefit from administering half the daily dose twice daily.

There are no controlled data to support the longer term use of RISPERDAL® beyond 8 weeks in adolescents with schizophrenia. The physician who elects to use RISPERDAL® for extended periods in adolescents with schizophrenia should periodically re-evaluate the long-term usefulness of the drug for the individual patient.

Reinitiation of Treatment in Patients Previously Discontinued

Although there are no data to specifically address reinitiation of treatment, it is recommended that after an interval off RISPERDAL®, the initial titration schedule should be followed.

Switching From Other Antipsychotics

There are no systematically collected data to specifically address switching schizophrenic patients from other antipsychotics to RISPERDAL®, or treating patients with concomitant antipsychotics. While immediate discontinuation of the previous antipsychotic treatment may be acceptable for some schizophrenic patients, more gradual discontinuation may be most appropriate for others. The period of overlapping antipsychotic administration should be minimized. When switching schizophrenic patients from depot antipsychotics, initiate RISPERDAL® therapy in place of the next scheduled injection. The need for continuing existing EPS medication should be re-evaluated periodically.

2.2 Bipolar Mania

Usual Dose

Adults

RISPERDAL® should be administered on a once-daily schedule, starting with 2 mg to 3 mg per day. Dosage adjustments, if indicated, should occur at intervals of not less than 24 hours and in dosage increments/decrements of 1 mg per day, as studied in the short-term, placebo-controlled trials. In these trials, short-term (3 week) anti-manic efficacy was demonstrated in a flexible dosage range of 1–6 mg per day [see Clinical Studies (14.2, 14.3)]. RISPERDAL® doses higher than 6 mg per day were not studied.

Pediatrics

The dosage of RISPERDAL® should be initiated at 0.5 mg once daily, administered as a single-daily dose in either the morning or evening. Dosage adjustments, if indicated, should occur at intervals not less than 24 hours, in increments of 0.5 or 1 mg/day, as tolerated, to a recommended dose of 2.5 mg/day. Although efficacy has been demonstrated in studies of pediatric patients with bipolar mania at doses between 0.5 and 6 mg/day, no additional benefit was seen above 2.5 mg/day, and higher doses were associated with more adverse events. Doses higher than 6 mg/day have not been studied.

Patients experiencing persistent somnolence may benefit from administering half the daily dose twice daily.

Maintenance Therapy

There is no body of evidence available from controlled trials to guide a clinician in the longer-term management of a patient who improves during treatment of an acute manic episode with RISPERDAL®. While it is generally agreed that pharmacological treatment beyond an acute response in mania is desirable, both for maintenance of the initial response and for prevention of new manic episodes, there are no systematically obtained data to support the use of RISPERDAL® in such longer-term treatment (i.e., beyond 3 weeks). The physician who elects to use RISPERDAL® for extended periods should periodically re-evaluate the long-term risks and benefits of the drug for the individual patient.

2.3 Irritability Associated with Autistic Disorder – Pediatrics (Children and Adolescents)

The safety and effectiveness of RISPERDAL® in pediatric patients with autistic disorder less than 5 years of age have not been established.

The dosage of RISPERDAL® should be individualized according to the response and tolerability of the patient. The total daily dose of RISPERDAL® can be administered once daily, or half the total daily dose can be administered twice daily.

Dosing should be initiated at 0.25 mg per day for patients < 20 kg and 0.5 mg per day for patients ≥ 20 kg. After a minimum of four days from treatment initiation, the dose may be increased to the recommended dose of 0.5 mg per day for patients < 20 kg and 1 mg per day for patients ≥ 20 kg. This dose should be maintained for a minimum of 14 days. In patients not achieving sufficient clinical response, dose increases may be considered at ≥ 2-week intervals in increments of 0.25 mg per day for patients < 20 kg or 0.5 mg per day for patients ≥ 20 kg. Caution should be exercised with dosage for smaller children who weigh less than 15 kg.

In clinical trials, 90% of patients who showed a response (based on at least 25% improvement on ABC-I, [see Clinical Studies (14.4)]) received doses of RISPERDAL® between 0.5 mg and 2.5 mg per day. The maximum daily dose of RISPERDAL® in one of the pivotal trials, when the therapeutic effect reached plateau, was 1 mg in patients < 20 kg, 2.5 mg in patients ≥ 20 kg, or 3 mg in patients > 45 kg. No dosing data is available for children who weighed less than 15 kg.

Once sufficient clinical response has been achieved and maintained, consideration should be given to gradually lowering the dose to achieve the optimal balance of efficacy and safety. The physician who elects to use RISPERDAL® for extended periods should periodically re-evaluate the long-term risks and benefits of the drug for the individual patient.

Patients experiencing persistent somnolence may benefit from a once-daily dose administered at bedtime or administering half the daily dose twice daily, or a reduction of the dose.

2.4 Dosage in Special Populations

The recommended initial dose is 0.5 mg twice daily in patients who are elderly or debilitated, patients with severe renal or hepatic impairment, and patients either predisposed to hypotension or for whom hypotension would pose a risk. Dosage increases in these patients should be in increments of no more than 0.5 mg twice daily. Increases to dosages above 1.5 mg twice daily should generally occur at intervals of at least 1 week. In some patients, slower titration may be medically appropriate.

Elderly or debilitated patients, and patients with renal impairment, may have less ability to eliminate RISPERDAL® than normal adults. Patients with impaired hepatic function may have increases in the free fraction of risperidone, possibly resulting in an enhanced effect [see Clinical Pharmacology (12.3)]. Patients with a predisposition to hypotensive reactions or for whom such reactions would pose a particular risk likewise need to be titrated cautiously and carefully monitored [see Warnings and Precautions (5.2, 5.7, 5.17)]. If a once-daily dosing regimen in the elderly or debilitated patient is being considered, it is recommended that the patient be titrated on a twice-daily regimen for 2–3 days at the target dose. Subsequent switches to a once-daily dosing regimen can be done thereafter.

2.5 Co-Administration of RISPERDAL® with Certain Other Medications

Co-administration of carbamazepine and other enzyme inducers (e.g., phenytoin, rifampin, phenobarbital) with RISPERDAL® would be expected to cause decreases in the plasma concentrations of the sum of risperidone and 9-hydroxyrisperidone combined, which could lead to decreased efficacy of RISPERDAL® treatment. The dose of RISPERDAL® needs to be titrated accordingly for patients receiving these enzyme inducers, especially during initiation or discontinuation of therapy with these inducers [see Drug Interactions (7.11)].

Fluoxetine and paroxetine have been shown to increase the plasma concentration of risperidone 2.5–2.8 fold and 3–9 fold, respectively. Fluoxetine did not affect the plasma concentration of 9-hydroxyrisperidone. Paroxetine lowered the concentration of 9-hydroxyrisperidone by about 10%. The dose of RISPERDAL® needs to be titrated accordingly when fluoxetine or paroxetine is co-administered [see Drug Interactions (7.10)].

2.6 Administration of RISPERDAL® Oral Solution

RISPERDAL® Oral Solution can be administered directly from the calibrated pipette, or can be mixed with a beverage prior to administration. RISPERDAL® Oral Solution is compatible in the following beverages: water, coffee, orange juice, and low-fat milk; it is NOT compatible with either cola or tea.

2.7 Directions for Use of RISPERDAL® M-TAB® Orally Disintegrating Tablets

Tablet Accessing

RISPERDAL® M-TAB® Orally Disintegrating Tablets 0.5 mg, 1 mg, and 2 mg

RISPERDAL® M-TAB® Orally Disintegrating Tablets 0.5 mg, 1 mg, and 2 mg are supplied in blister packs of 4 tablets each.

Do not open the blister until ready to administer. For single tablet removal, separate one of the four blister units by tearing apart at the perforations. Bend the corner where indicated. Peel back foil to expose the tablet. DO NOT push the tablet through the foil because this could damage the tablet.

RISPERDAL® M-TAB® Orally Disintegrating Tablets 3 mg and 4 mg

RISPERDAL® M-TAB® Orally Disintegrating Tablets 3 mg and 4 mg are supplied in a child-resistant pouch containing a blister with 1 tablet each.

The child-resistant pouch should be torn open at the notch to access the blister. Do not open the blister until ready to administer. Peel back foil from the side to expose the tablet. DO NOT push the tablet through the foil, because this could damage the tablet.

Tablet Administration

Using dry hands, remove the tablet from the blister unit and immediately place the entire RISPERDAL® M-TAB® Orally Disintegrating Tablet on the tongue. The RISPERDAL® M-TAB® Orally Disintegrating Tablet should be consumed immediately, as the tablet cannot be stored once removed from the blister unit. RISPERDAL® M-TAB® Orally Disintegrating Tablets disintegrate in the mouth within seconds and can be swallowed subsequently with or without liquid. Patients should not attempt to split or to chew the tablet.

3 DOSAGE FORMS AND STRENGTHS

RISPERDAL® Tablets are available in the following strengths and colors: 0.25 mg (dark yellow), 0.5 mg (red-brown), 1 mg (white), 2 mg (orange), 3 mg (yellow), and 4 mg (green). All are capsule shaped, and imprinted with "JANSSEN" on one side and either "Ris 0.25", "Ris 0.5", "R1", "R2", "R3", or "R4" on the other side according to their respective strengths.

RISPERDAL® Oral Solution is available in a 1 mg/mL strength.

RISPERDAL® M-TAB® Orally Disintegrating Tablets are available in the following strengths, colors, and shapes: 0.5 mg (light coral, round), 1 mg (light coral, square), 2 mg (coral, square), 3 mg (coral, round), and 4 mg (coral, round). All are biconvex and etched on one side with "R0.5", "R1", "R2", "R3", or "R4" according to their respective strengths.

4 CONTRAINDICATIONS

Hypersensitivity reactions, including anaphylactic reactions and angioedema, have been observed in patients treated with risperidone. Therefore, RISPERDAL® is contraindicated in patients with a known hypersensitivity to the product.

5 WARNINGS AND PRECAUTIONS

5.1 Increased Mortality in Elderly Patients with Dementia-Related Psychosis

Elderly patients with dementia-related psychosis treated with antipsychotic drugs are at an increased risk of death. RISPERDAL® (risperidone) is not approved for the treatment of dementia-related psychosis [see Boxed Warning].

5.2 Cerebrovascular Adverse Events, Including Stroke, in Elderly Patients with Dementia-Related Psychosis

Cerebrovascular adverse events (e.g., stroke, transient ischemic attack), including fatalities, were reported in patients (mean age 85 years; range 73–97) in trials of risperidone in elderly patients with dementia-related psychosis. In placebo-controlled trials, there was a significantly higher incidence of cerebrovascular adverse events in patients treated with risperidone compared to patients treated with placebo. RISPERDAL® is not approved for the treatment of patients with dementia-related psychosis. [See also Boxed Warnings and Warnings and Precautions (5.1)]

5.3 Neuroleptic Malignant Syndrome (NMS)

A potentially fatal symptom complex sometimes referred to as Neuroleptic Malignant Syndrome (NMS) has been reported in association with antipsychotic drugs. Clinical manifestations of NMS are hyperpyrexia, muscle rigidity, altered mental status, and evidence of autonomic instability (irregular pulse or blood pressure, tachycardia, diaphoresis, and cardiac dysrhythmia). Additional signs may include elevated creatine phosphokinase, myoglobinuria (rhabdomyolysis), and acute renal failure.

The diagnostic evaluation of patients with this syndrome is complicated. In arriving at a diagnosis, it is important to identify cases in which the clinical presentation includes both serious medical illness (e.g., pneumonia, systemic infection, etc.) and untreated or inadequately treated extrapyramidal signs and symptoms (EPS). Other important considerations in the differential diagnosis include central anticholinergic toxicity, heat stroke, drug fever, and primary central nervous system pathology.

The management of NMS should include: (1) immediate discontinuation of antipsychotic drugs and other drugs not essential to concurrent therapy; (2) intensive symptomatic treatment and medical monitoring; and (3) treatment of any concomitant serious medical problems for which specific treatments are available. There is no general agreement about specific pharmacological treatment regimens for uncomplicated NMS.

If a patient requires antipsychotic drug treatment after recovery from NMS, the potential reintroduction of drug therapy should be carefully considered. The patient should be carefully monitored, since recurrences of NMS have been reported.

5.4 Tardive Dyskinesia

A syndrome of potentially irreversible, involuntary, dyskinetic movements may develop in patients treated with antipsychotic drugs. Although the prevalence of the syndrome appears to be highest among the elderly, especially elderly women, it is impossible to rely upon prevalence estimates to predict, at the inception of antipsychotic treatment, which patients are likely to develop the syndrome. Whether antipsychotic drug products differ in their potential to cause tardive dyskinesia is unknown.

The risk of developing tardive dyskinesia and the likelihood that it will become irreversible are believed to increase as the duration of treatment and the total cumulative dose of antipsychotic drugs administered to the patient increase. However, the syndrome can develop, although much less commonly, after relatively brief treatment periods at low doses.

There is no known treatment for established cases of tardive dyskinesia, although the syndrome may remit, partially or completely, if antipsychotic treatment is withdrawn. Antipsychotic treatment, itself, however, may suppress (or partially suppress) the signs and symptoms of the syndrome and thereby may possibly mask the underlying process. The effect that symptomatic suppression has upon the long-term course of the syndrome is unknown.

Given these considerations, RISPERDAL® should be prescribed in a manner that is most likely to minimize the occurrence of tardive dyskinesia. Chronic antipsychotic treatment should generally be reserved for patients who suffer from a chronic illness that: (1) is known to respond to antipsychotic drugs, and (2) for whom alternative, equally effective, but potentially less harmful treatments are not available or appropriate. In patients who do require chronic treatment, the smallest dose and the shortest duration of treatment producing a satisfactory clinical response should be sought. The need for continued treatment should be reassessed periodically.

If signs and symptoms of tardive dyskinesia appear in a patient treated with RISPERDAL®, drug discontinuation should be considered. However, some patients may require treatment with RISPERDAL® despite the presence of the syndrome.

5.5 Hyperglycemia and Diabetes Mellitus

Hyperglycemia, in some cases extreme and associated with ketoacidosis or hyperosmolar coma or death, has been reported in patients treated with atypical antipsychotics including RISPERDAL®. Assessment of the relationship between atypical antipsychotic use and glucose abnormalities is complicated by the possibility of an increased background risk of diabetes mellitus in patients with schizophrenia and the increasing incidence of diabetes mellitus in the general population. Given these confounders, the relationship between atypical antipsychotic use and hyperglycemia-related adverse events is not completely understood. However, epidemiological studies suggest an increased risk of treatment-emergent hyperglycemia-related adverse events in patients treated with the atypical antipsychotics. Precise risk estimates for hyperglycemia-related adverse events in patients treated with atypical antipsychotics are not available.

Patients with an established diagnosis of diabetes mellitus who are started on atypical antipsychotics should be monitored regularly for worsening of glucose control. Patients with risk factors for diabetes mellitus (e.g., obesity, family history of diabetes) who are starting treatment with atypical antipsychotics should undergo fasting blood glucose testing at the beginning of treatment and periodically during treatment. Any patient treated with atypical antipsychotics should be monitored for symptoms of hyperglycemia including polydipsia, polyuria, polyphagia, and weakness. Patients who develop symptoms of hyperglycemia during treatment with atypical antipsychotics should undergo fasting blood glucose testing. In some cases, hyperglycemia has resolved when the atypical antipsychotic was discontinued; however, some patients required continuation of anti-diabetic treatment despite discontinuation of the suspect drug.

5.6 Hyperprolactinemia

As with other drugs that antagonize dopamine D2 receptors, RISPERDAL® elevates prolactin levels and the elevation persists during chronic administration. RISPERDAL® is associated with higher levels of prolactin elevation than other antipsychotic agents.

Hyperprolactinemia may suppress hypothalamic GnRH, resulting in reduced pituitary gonadotropin secretion. This, in turn, may inhibit reproductive function by impairing gonadal steroidogenesis in both female and male patients. Galactorrhea, amenorrhea, gynecomastia, and impotence have been reported in patients receiving prolactin-elevating compounds. Long-standing hyperprolactinemia when associated with hypogonadism may lead to decreased bone density in both female and male subjects.

Tissue culture experiments indicate that approximately one-third of human breast cancers are prolactin dependent in vitro, a factor of potential importance if the prescription of these drugs is contemplated in a patient with previously detected breast cancer. An increase in pituitary gland, mammary gland, and pancreatic islet cell neoplasia (mammary adenocarcinomas, pituitary and pancreatic adenomas) was observed in the risperidone carcinogenicity studies conducted in mice and rats [see Non-Clinical Toxicology (13.1)]. Neither clinical studies nor epidemiologic studies conducted to date have shown an association between chronic administration of this class of drugs and tumorigenesis in humans; the available evidence is considered too limited to be conclusive at this time.

5.7 Orthostatic Hypotension

RISPERDAL® may induce orthostatic hypotension associated with dizziness, tachycardia, and in some patients, syncope, especially during the initial dose-titration period, probably reflecting its alpha-adrenergic antagonistic properties. Syncope was reported in 0.2% (6/2607) of RISPERDAL®-treated patients in Phase 2 and 3 studies in adults with schizophrenia. The risk of orthostatic hypotension and syncope may be minimized by limiting the initial dose to 2 mg total (either once daily or 1 mg twice daily) in normal adults and 0.5 mg twice daily in the elderly and patients with renal or hepatic impairment [see Dosage and Administration (2.1, 2.4)]. Monitoring of orthostatic vital signs should be considered in patients for whom this is of concern. A dose reduction should be considered if hypotension occurs. RISPERDAL® should be used with particular caution in patients with known cardiovascular disease (history of myocardial infarction or ischemia, heart failure, or conduction abnormalities), cerebrovascular disease, and conditions which would predispose patients to hypotension, e.g., dehydration and hypovolemia. Clinically significant hypotension has been observed with concomitant use of RISPERDAL® and antihypertensive medication.

5.8 Leukopenia, Neutropenia, and Agranulocytosis

Class Effect: In clinical trial and/or postmarketing experience, events of leukopenia/neutropenia have been reported temporally related to antipsychotic agents, including RISPERDAL®. Agranulocytosis has also been reported.

Possible risk factors for leukopenia/neutropenia include pre-existing low white blood cell count (WBC) and history of drug-induced leukopenia/neutropenia. Patients with a history of a clinically significant low WBC or a drug-induced leukopenia/neutropenia should have their complete blood count (CBC) monitored frequently during the first few months of therapy and discontinuation of RISPERDAL® should be considered at the first sign of a clinically significant decline in WBC in the absence of other causative factors.

Patients with clinically significant neutropenia should be carefully monitored for fever or other symptoms or signs of infection and treated promptly if such symptoms or signs occur. Patients with severe neutropenia (absolute neutrophil count <1000/mm^3) should discontinue RISPERDAL® and have their WBC followed until recovery.

5.9 Potential for Cognitive and Motor Impairment

Somnolence was a commonly reported adverse event associated with RISPERDAL® treatment, especially when ascertained by direct questioning of patients. This adverse event is dose-related, and in a study utilizing a checklist to detect adverse events, 41% of the high-dose patients (RISPERDAL® 16 mg/day) reported somnolence compared to 16% of placebo patients. Direct questioning is more sensitive for detecting adverse events than spontaneous reporting, by which 8% of RISPERDAL® 16 mg/day patients and 1% of placebo patients reported somnolence as an adverse event. Since RISPERDAL® has the potential to impair judgment, thinking, or motor skills, patients should be cautioned about operating hazardous machinery, including automobiles, until they are reasonably certain that RISPERDAL® therapy does not affect them adversely.

5.10 Seizures

During premarketing testing in adult patients with schizophrenia, seizures occurred in 0.3% (9/2607) of RISPERDAL®-treated patients, two in association with hyponatremia. RISPERDAL® should be used cautiously in patients with a history of seizures.

5.11 Dysphagia

Esophageal dysmotility and aspiration have been associated with antipsychotic drug use. Aspiration pneumonia is a common cause of morbidity and mortality in patients with advanced Alzheimer's dementia. RISPERDAL® and other antipsychotic drugs should be used cautiously in patients at risk for aspiration pneumonia. [See also Boxed Warning and Warnings and Precautions (5.1)]

5.12 Priapism

Rare cases of priapism have been reported. While the relationship of the events to RISPERDAL® use has not been established, other drugs with alpha-adrenergic blocking effects have been reported to induce priapism, and it is possible that RISPERDAL® may share this capacity. Severe priapism may require surgical intervention.

5.13 Thrombotic Thrombocytopenic Purpura (TTP)

A single case of TTP was reported in a 28 year-old female patient receiving oral RISPERDAL® in a large, open premarketing experience (approximately 1300 patients). She experienced jaundice, fever, and bruising, but eventually recovered after receiving plasmapheresis. The relationship to RISPERDAL® therapy is unknown.

5.14 Body Temperature Regulation

Disruption of body temperature regulation has been attributed to antipsychotic agents. Both hyperthermia and hypothermia have been reported in association with oral RISPERDAL® use. Caution is advised when prescribing for patients who will be exposed to temperature extremes.

5.15 Antiemetic Effect

Risperidone has an antiemetic effect in animals; this effect may also occur in humans, and may mask signs and symptoms of overdosage with certain drugs or of conditions such as intestinal obstruction, Reye's syndrome, and brain tumor.

5.16 Suicide

The possibility of a suicide attempt is inherent in patients with schizophrenia and bipolar mania, including children and adolescent patients, and close supervision of high-risk patients should accompany drug therapy. Prescriptions for RISPERDAL® should be written for the smallest quantity of tablets, consistent with good patient management, in order to reduce the risk of overdose.

5.17 Use in Patients with Concomitant Illness

Clinical experience with RISPERDAL® in patients with certain concomitant systemic illnesses is limited. Patients with Parkinson's Disease or Dementia with Lewy Bodies who receive antipsychotics, including RISPERDAL®, are reported to have an increased sensitivity to antipsychotic medications. Manifestations of this increased sensitivity have been reported to include confusion, obtundation, postural instability with frequent falls, extrapyramidal symptoms, and clinical features consistent with the neuroleptic malignant syndrome.

Caution is advisable in using RISPERDAL® in patients with diseases or conditions that could affect metabolism or hemodynamic responses. RISPERDAL® has not been evaluated or used to any appreciable extent in patients with a recent history of myocardial infarction or unstable heart disease. Patients with these diagnoses were excluded from clinical studies during the product's premarket testing.

Increased plasma concentrations of risperidone and 9-hydroxyrisperidone occur in patients with severe renal impairment (creatinine clearance <30 mL/min/1.73 m^2), and an increase in the free fraction of risperidone is seen in patients with severe hepatic impairment. A lower starting dose should be used in such patients [see Dosage and Administration (2.4)].

5.18 Monitoring: Laboratory Tests

No specific laboratory tests are recommended.

6 ADVERSE REACTIONS

The following are discussed in more detail in other sections of the labeling:

- Increased mortality in elderly patients with dementia-related psychosis [see Boxed Warning and Warnings and Precautions (5.1)]
- Cerebrovascular adverse events, including stroke, in elderly patients with dementia-related psychosis [see Warnings and Precautions (5.2)]
- Neuroleptic malignant syndrome [see Warnings and Precautions (5.3)]
- Tardive dyskinesia [see Warnings and Precautions (5.4)]
- Hyperglycemia and diabetes mellitus [see Warnings and Precautions (5.5)]
- Hyperprolactinemia [see Warnings and Precautions (5.6)]
- Orthostatic hypotension [see Warnings and Precautions (5.7)]
- Leukopenia, neutropenia, and agranulocytosis [see Warnings and Precautions (5.8)]
- Potential for cognitive and motor impairment [see Warnings and Precautions (5.9)]
- Seizures [see Warnings and Precautions (5.10)]
- Dysphagia [see Warnings and Precautions (5.11)]
- Priapism [see Warnings and Precautions (5.12)]
- Thrombotic Thrombocytopenic Purpura (TTP) [see Warnings and Precautions (5.13)]
- Disruption of body temperature regulation [see Warnings and Precautions (5.14)]
- Antiemetic effect [see Warnings and Precautions (5.15)]
- Suicide [see Warnings and Precautions (5.16)]
- Increased sensitivity in patients with Parkinson's disease or those with dementia with Lewy bodies [see Warnings and Precautions (5.17)]
- Diseases or conditions that could affect metabolism or hemodynamic responses [see Warnings and Precautions (5.17)]

The most common adverse reactions in clinical trials (≥ 10%) were somnolence, appetite increased, fatigue, rhinitis, upper respiratory tract infection, vomiting, coughing, urinary incontinence, saliva increased, constipation, fever, Parkinsonism, dystonia, abdominal pain, anxiety, nausea, dizziness, dry mouth, tremor, rash, akathisia, and dyspepsia.

The most common adverse reactions that were associated with discontinuation from clinical trials (causing discontinuation in >1% of adults and/or >2% of pediatrics) were somnolence, nausea, abdominal pain, dizziness, vomiting, agitation, and akathisia [see Adverse Reactions (6.5)].

The data described in this section are derived from a clinical trial database consisting of 9712 adult and pediatric patients exposed to one or more doses of RISPERDAL® for the treatment of schizophrenia, bipolar mania, autistic disorder, and other psychiatric disorders in pediatrics and elderly patients with dementia. Of these 9712 patients, 2626 were patients who received RISPERDAL® while participating in double-blind, placebo-controlled trials. The conditions and duration of treatment with RISPERDAL® varied greatly and included (in overlapping categories) double-blind, fixed- and flexible-dose, placebo- or active-controlled studies and open-label phases of studies, inpatients and outpatients, and short-term (up to 12 weeks) and longer-term (up to 3 years) exposures. Safety was assessed by collecting adverse events and performing physical examinations, vital signs, body weights, laboratory analyses, and ECGs.

Adverse events during exposure to study treatment were obtained by general inquiry and recorded by clinical investigators using their own terminology. Consequently, to provide a meaningful estimate of the proportion of individuals experiencing adverse events, events were grouped in standardized categories using WHOART terminology.

Throughout this section, adverse reactions are reported. Adverse reactions are adverse events that were considered to be reasonably associated with the use of RISPERDAL® (adverse drug reactions) based on the comprehensive assessment of the available adverse event information. A causal association for RISPERDAL® often cannot be reliably established in individual cases. Further, because clinical trials are conducted under widely varying conditions, adverse reaction rates observed in the clinical trials of a drug cannot be directly compared to rates in the clinical trials of another drug and may not reflect the rates observed in clinical practice.

The majority of all adverse reactions were mild to moderate in severity.

6.1 Commonly-Observed Adverse Reactions in Double-Blind, Placebo-Controlled Clinical Trials - Schizophrenia

Adult Patients with Schizophrenia

Table 1 lists the adverse reactions reported in 1% or more of RISPERDAL®-treated adult patients with schizophrenia in three 4- to 8-week, double-blind, placebo-controlled trials.

Table 1. Adverse Reactions in ≥1% of RISPERDAL®-Treated Adult Patients with Schizophrenia in Double-Blind, Placebo-Controlled Trials
 | Percentage of Patients Reporting Event
 | RISPERDAL®
Body System Adverse Reaction | 2–8 mg per day (N=366) | >8–16 mg per day (N=198) | Placebo (N=225)
Body as a whole - general disorders
Back pain | 3 | 2 | <1
Fatigue | 3 | 1 | 0
Chest pain | 3 | 1 | 2
Fever | 2 | 1 | 1
Asthenia | 1 | 1 | <1
Syncope | <1 | 1 | <1
Edema | <1 | 1 | 0
Cardiovascular disorders, general
Hypotension postural | 2 | <1 | 0
Hypotension | <1 | 1 | 0
Central and peripheral nervous system disorders
Parkinsonism [Parkinsonism includes extrapyramidal disorder, hypokinesia, and bradycardia. Dystonia includes dystonia, hypertonia, oculogyric crisis, muscle contractions involuntary, tetany, laryngismus, tongue paralysis, and torticollis. Akathisia includes hyperkinesia and akathisia.] | 12 | 17 | 6
Dizziness | 10 | 4 | 2
Dystonia | 5 | 5 | 2
Akathisia | 5 | 5 | 2
Dyskinesia | 1 | 1 | <1
Gastrointestinal system disorders
Dyspepsia | 10 | 7 | 6
Nausea | 9 | 4 | 4
Constipation | 8 | 9 | 7
Abdominal pain | 4 | 3 | 0
Mouth dry | 4 | <1 | <1
Saliva increased | 3 | 1 | <1
Diarrhea | 2 | <1 | 1
Hearing and vestibular disorders
Earache | 1 | 1 | 0
Heart rate and rhythm disorders
Tachycardia | 2 | 5 | 0
Arrhythmia | 0 | 1 | 0
Metabolic and nutritional disorders
Weight increase | 1 | <1 | 0
Creatine phosphokinase increased | <1 | 2 | <1
Musculoskeletal system disorders
Arthralgia | 2 | 3 | <1
Myalgia | 1 | 0 | 0
Platelet, bleeding and clotting disorders
Epistaxis | <1 | 2 | 0
Psychiatric disorders
Anxiety | 16 | 12 | 11
Somnolence | 14 | 5 | 4
Anorexia | 2 | 0 | <1
Red blood cell disorders
Anemia | <1 | 1 | 0
Reproductive disorders, male
Ejaculation failure | <1 | 1 | 0
Respiratory system disorders
Rhinitis | 7 | 11 | 6
Coughing | 3 | 3 | 3
Upper respiratory tract infection | 2 | 3 | <1
Dyspnea | 2 | 2 | 0
Skin and appendages disorders
Rash | 2 | 4 | 2
Seborrhea | <1 | 2 | 0
Urinary system disorders
Urinary tract infection | <1 | 3 | 0
Vision disorders
Vision abnormal | 3 | 1 | <1

Pediatric Patients with Schizophrenia

Table 2 lists the adverse reactions reported in 5% or more of RISPERDAL®-treated pediatric patients with schizophrenia in a 6-week double-blind, placebo-controlled trial.

Table 2. Adverse Reactions in ≥5% of RISPERDAL®-Treated Pediatric Patients with Schizophrenia in a Double-Blind Trial
 | Percentage of Patients Reporting Event
 | RISPERDAL®
Body System Adverse Reaction | 1–3 mg per day (N=55) | 4–6 mg per day (N=51) | Placebo (N=54)
Central and peripheral nervous system disorders
Parkinsonism [Parkinsonism includes extrapyramidal disorder, hypokinesia, and bradykinesia. Dystonia includes dystonia, hypertonia, oculogyric crisis, muscle contractions involuntary, tetany, laryngismus, tongue paralysis, and torticollis. Akathisia includes hyperkinesia and akathisia.] | 13 | 16 | 6
Tremor | 11 | 10 | 6
Dystonia | 9 | 18 | 7
Dizziness | 7 | 14 | 2
Akathisia | 7 | 10 | 6
Gastrointestinal system disorders
Saliva increased | 0 | 10 | 2
Psychiatric disorders
Somnolence | 24 | 12 | 4
Anxiety | 7 | 6 | 0

6.2 Commonly-Observed Adverse Reactions in Double-Blind, Placebo-Controlled Clinical Trials – Bipolar Mania

Adult Patients with Bipolar Mania

Table 3 lists the adverse reactions reported in 1% or more of RISPERDAL®-treated adult patients with bipolar mania in four 3-week, double-blind, placebo-controlled monotherapy trials.

Table 3. Adverse Reactions in ≥1% of RISPERDAL®-Treated Adult Patients with Bipolar Mania in Double-Blind, Placebo-Controlled Monotherapy Trials
 | Percentage of Patients Reporting Event
Body System Adverse Reaction | RISPERDAL® 1–6 mg per day (N=448) | Placebo (N=424)
Body as a whole - general disorders
Fatigue | 2 | <1
Fever | 1 | <1
Asthenia | 1 | <1
Edema | 1 | <1
Central and peripheral nervous system disorders
Parkinsonism [Parkinsonism includes extrapyramidal disorder, hypokinesia, and bradycardia. Dystonia includes dystonia, hypertonia, oculogyric crisis, muscle contractions involuntary, tetany, laryngismus, tongue paralysis, and torticollis. Akathisia includes hyperkinesia and akathisia.] | 20 | 6
Dystonia | 11 | 3
Akathisia | 9 | 3
Tremor | 6 | 4
Dizziness | 5 | 5
Gastrointestinal system disorders
Nausea | 5 | 2
Dyspepsia | 4 | 2
Saliva increased | 3 | <1
Diarrhea | 3 | 2
Mouth dry | 1 | 1
Heart rate and rhythm disorders
Tachycardia | 1 | <1
Liver and biliary system disorders
SGOT increased | 1 | <1
Musculoskeletal disorders
Myalgia | 2 | 2
Psychiatric disorders
Somnolence | 12 | 4
Anxiety | 2 | 2
Reproductive disorders, female
Lactation nonpuerperal | 1 | 0
Respiratory disorders
Rhinitis | 2 | 2
Skin and appendages disorders
Acne | 1 | 0
Vision disorders
Vision abnormal | 2 | <1

Table 4 lists the adverse reactions reported in 2% or more of RISPERDAL®-treated adult patients with bipolar mania in two 3-week, double-blind, placebo-controlled adjuvant therapy trials.

Table 4. Adverse Reactions in ≥2% of RISPERDAL®-Treated Adult Patients with Bipolar Mania in Double-Blind, Placebo-Controlled Adjuvant Therapy Trials
 | Percentage of Patients Reporting Event
Body System Adverse Reaction | RISPERDAL® + Mood Stabilizer (N=127) | Placebo + Mood Stabilizer (N=126)
Body as a whole – general disorders
Chest pain | 2 | 2
Fatigue | 2 | 2
Central and peripheral nervous system disorders
Parkinsonism [Parkinsonism includes extrapyramidal disorder, hypokinesia and bradykinesia. Dystonia includes dystonia, hypertonia, oculogyric crisis, muscle contractions involuntary, tetany, laryngismus, tongue paralysis, and torticollis. Akathisia includes hyperkinesia and akathisia.] | 9 | 4
Dizziness | 8 | 2
Dystonia | 6 | 3
Akathisia | 6 | 0
Tremor | 5 | 2
Gastrointestinal system disorders
Nausea | 6 | 5
Diarrhea | 6 | 4
Saliva increased | 4 | 0
Abdominal pain | 2 | 0
Heart rate and rhythm disorders
Palpitation | 2 | 0
Metabolic and nutritional disorders
Weight increase | 2 | 2
Psychiatric disorders
Somnolence | 12 | 5
Anxiety | 4 | 2
Respiratory disorders
Pharyngitis | 5 | 2
Coughing | 3 | 1
Skin and appendages disorders
Rash | 2 | 2
Urinary system disorders
Urinary incontinence | 2 | 1
Urinary tract infection | 2 | 1

Pediatric Patients with Bipolar Mania

Table 5 lists the adverse reactions reported in 5% or more of RISPERDAL®-treated pediatric patients with bipolar mania in a 3-week double-blind, placebo-controlled trial.

Table 5. Adverse Reactions in ≥5% of RISPERDAL®-Treated Pediatric Patients with Bipolar Mania in Double-Blind, Placebo-Controlled Trials
 | Percentage of Patients Reporting Event
 | RISPERDAL ®
Body System Adverse Reaction | 0.5–2.5 mg per day (N=50) | 3–6 mg per day (N=61) | Placebo (N=58)
Body as a whole - general disorders
Fatigue | 18 | 30 | 3
Central and peripheral nervous system disorders
Dizziness | 16 | 13 | 5
Dystonia [Dystonia includes dystonia, hypertonia, oculogyric crisis, muscle contractions involuntary, tetany, laryngismus, tongue paralysis, and torticollis. Parkinsonism includes extrapyramidal disorder, hypokinesia, and bradykinesia. Akathisia includes hyperkinesia and akathisia.] | 8 | 13 | 2
Parkinsonism | 2 | 7 | 2
Akathisia | 0 | 7 | 2
Gastrointestinal system disorders
Abdominal pain | 18 | 15 | 5
Dyspepsia | 16 | 5 | 3
Nausea | 16 | 13 | 7
Vomiting | 12 | 10 | 7
Diarrhea | 8 | 7 | 2
Heart rate and rhythm disorders
Tachycardia | 0 | 5 | 2
Psychiatric disorders
Somnolence | 42 | 56 | 19
Appetite increased | 4 | 7 | 2
Anxiety | 0 | 8 | 3
Reproductive disorders, female
Lactation nonpuerperal | 2 | 5 | 0
Respiratory system disorders
Rhinitis | 14 | 13 | 10
Dyspnea | 2 | 5 | 0
Skin and appendages disorders
Rash | 0 | 7 | 2
Urinary system disorders
Urinary incontinence | 0 | 5 | 0
Vision disorders
Vision abnormal | 4 | 7 | 0

6.3 Commonly-Observed Adverse Reactions in Double-Blind, Placebo-Controlled Clinical Trials - Autistic Disorder

Table 6 lists the adverse reactions reported in 5% or more of RISPERDAL®-treated pediatric patients treated for irritability associated with autistic disorder in two 8-week, double-blind, placebo-controlled trials.

Table 6. Adverse Reactions in ≥5% of RISPERDAL®-Treated Pediatric Patients Treated for Irritability Associated with Autistic Disorder in Double-Blind, Placebo-Controlled Trials
 | Percentage of Patients Reporting Event
Body System Adverse Reaction | RISPERDAL® 0.5–4.0 mg per day (N=76) | Placebo (N=80)
Body as a whole - general disorders
Fatigue | 42 | 13
Fever | 20 | 19
Central and peripheral nervous system disorders
Dystonia [Dystonia includes dystonia, hypertonia, oculogyric crisis, muscle contractions involuntary, tetany, laryngismus, tongue paralysis, and torticollis. Parkinsonism includes extrapyramidal disorder, hypokinesia, and bradycardia.] | 12 | 6
Tremor | 12 | 1
Dizziness | 9 | 3
Parkinsonism | 8 | 0
Automatism | 7 | 1
Dyskinesia | 7 | 0
Gastrointestinal system disorders
Vomiting | 25 | 21
Saliva increased | 22 | 6
Constipation | 21 | 8
Mouth dry | 13 | 6
Nausea | 8 | 8
Heart rate and rhythm disorders
Tachycardia | 7 | 0
Metabolic and nutritional disorders
Weight increase | 5 | 0
Psychiatric disorders
Somnolence | 67 | 23
Appetite increased | 49 | 19
Anxiety | 16 | 15
Anorexia | 8 | 8
Confusion | 5 | 0
Respiratory system disorders
Rhinitis | 36 | 23
Upper respiratory tract infection | 34 | 15
Coughing | 24 | 18
Skin and appendages disorders
Rash | 11 | 8
Urinary system disorders
Urinary incontinence | 22 | 20

6.4 Other Adverse Reactions Observed During the Premarketing Evaluation of RISPERDAL®

The following adverse reactions occurred in < 1% of the adult patients and in < 5% of the pediatric patients treated with RISPERDAL® in the above double-blind, placebo-controlled clinical trial data sets. In addition, the following also includes adverse reactions reported in RISPERDAL®-treated patients who participated in other studies, including double-blind, active-controlled and open-label studies in schizophrenia and bipolar mania studies in pediatric patients with psychiatric disorders other than schizophrenia, bipolar mania, or autistic disorder, and studies in elderly patients with dementia.

Body as a Whole, General Disorders: edema peripheral, pain, influenza-like symptoms, leg pain, malaise, allergy, crying abnormal, allergic reaction, rigors, allergy aggravated, anaphylactoid reaction, hypothermia

Central Nervous System Disorders: gait abnormal, speech disorder, coma, ataxia, dysphonia, stupor, cramps legs, vertigo, hypoesthesia, tardive dyskinesia, neuroleptic malignant syndrome

Endocrine Disorders: hyperprolactinemia, gynecomastia

Gastrointestinal System Disorders: dysphagia, flatulence

Heart Rate and Rhythm Disorders: AV block, bundle branch block

Liver and Biliary Disorders: SGPT increased, hepatic enzymes increased

Metabolic and Nutritional Disorders: thirst, hyperglycemia, xerophthalmia, generalized edema, diabetes mellitus aggravated, diabetic coma

Musculoskeletal Disorders: muscle weakness, rhabdomyolysis

Platelet, Bleeding, and Clotting Disorders: purpura

Psychiatric Disorders: insomnia, agitation, emotional lability, apathy, nervousness, concentration impaired, impotence, decreased libido

Reproductive Disorders, Female: amenorrhea, menstrual disorder, leukorrhea

Reproductive Disorders, Male: ejaculation disorder, abnormal sexual function, priapism

Resistance Mechanism Disorders: otitis media, viral infection

Respiratory Disorders: respiratory disorder

Skin and Appendages Disorders: skin ulceration, skin discoloration, rash erythematous, skin exfoliation, rash maculopapular, erythema multiforme

Urinary Disorders: micturition frequency

Vascular Disorders: cerebrovascular disorder

Vision Disorders: conjunctivitis

White Cell Disorders: leucopenia, granulocytopenia

6.5 Discontinuations Due to Adverse Reactions

Schizophrenia - Adults

Approximately 7% (39/564) of RISPERDAL®-treated patients in double-blind, placebo-controlled trials discontinued treatment due to an adverse event, compared with 4% (10/225) who were receiving placebo. The adverse reactions associated with discontinuation in 2 or more RISPERDAL®-treated patients were:

Table 7. Adverse Reactions Associated With Discontinuation in 2 or More RISPERDAL®-Treated Adult Patients in Schizophrenia Trials
 | RISPERDAL®
Adverse Reaction | 2–8 mg/day (N=366) | >8–16 mg/day (N=198) | Placebo (N=225)
Dizziness | 1.4% | 1.0% | 0%
Nausea | 1.4% | 0% | 0%
Agitation | 1.1% | 1.0% | 0%
Parkinsonism | 0.8% | 0% | 0%
Somnolence | 0.8% | 0.5% | 0%
Dystonia | 0.5% | 0% | 0%
Abdominal pain | 0.5% | 0% | 0%
Hypotension postural | 0.3% | 0.5% | 0%
Tachycardia | 0.3% | 0.5% | 0%
Akathisia | 0% | 1.0% | 0%

Discontinuation for extrapyramidal symptoms (including Parkinsonism, akathisia, dystonia, and tardive dyskinesia) was 1% in placebo-treated patients, and 3.4% in active control-treated patients in a double-blind, placebo- and active-controlled trial.

Schizophrenia - Pediatrics

Approximately 7% (7/106), of RISPERDAL®-treated patients discontinued treatment due to an adverse event in a double-blind, placebo-controlled trial, compared with 4% (2/54) placebo-treated patients. The adverse reactions associated with discontinuation for at least one RISPERDAL®-treated patient were somnolence (2%), dizziness (2%), anorexia (1%), anxiety (1%), ataxia (1%), hypotension (1%), and palpitation (1%).

Bipolar Mania - Adults

In double-blind, placebo-controlled trials with RISPERDAL® as monotherapy, approximately 6% (25/448) of RISPERDAL®-treated patients discontinued treatment due to an adverse event, compared with approximately 5% (19/424) of placebo-treated patients. The adverse reactions associated with discontinuation in RISPERDAL®-treated patients were:

Table 8. Adverse Reactions Associated With Discontinuation in 2 or More RISPERDAL®-Treated Adult Patients in Bipolar Mania Clinical Trials
Adverse Reaction | RISPERDAL® 1–6 mg/day (N=448) | Placebo (N=424)
Parkinsonism | 0.4% | 0%
Somnolence | 0.2% | 0%
Dizziness | 0.2% | 0%
Dystonia | 0.2% | 0%
SGOT increased | 0.2% | 0.2%
SGPT increased | 0.2% | 0.2%

Bipolar Mania - Pediatrics

In a double-blind, placebo-controlled trial 12% (13/111) of RISPERDAL®-treated patients discontinued due to an adverse event, compared with 7% (4/58) of placebo-treated patients. The adverse reactions associated with discontinuation in more than one RISPERDAL®-treated pediatric patient were somnolence (5%), nausea (3%), abdominal pain (2%), and vomiting (2%).

Autistic Disorder - Pediatrics

In the two 8-week, placebo-controlled trials in pediatric patients treated for irritability associated with autistic disorder (n = 156), one RISPERDAL®-treated patient discontinued due to an adverse reaction (Parkinsonism), and one placebo-treated patient discontinued due to an adverse event.

6.6 Dose Dependency of Adverse Reactions in Clinical Trials

Extrapyramidal Symptoms

Data from two fixed-dose trials in adults with schizophrenia provided evidence of dose-relatedness for extrapyramidal symptoms associated with RISPERDAL® treatment.

Two methods were used to measure extrapyramidal symptoms (EPS) in an 8-week trial comparing 4 fixed doses of RISPERDAL® (2, 6, 10, and 16 mg/day), including (1) a Parkinsonism score (mean change from baseline) from the Extrapyramidal Symptom Rating Scale, and (2) incidence of spontaneous complaints of EPS:

Dose Groups | Placebo | RISPERDAL® 2 mg | RISPERDAL® 6 mg | RISPERDAL® 10 mg | RISPERDAL® 16 mg
Parkinsonism | 1.2 | 0.9 | 1.8 | 2.4 | 2.6
EPS Incidence | 11% | 15% | 16% | 20% | 31%

Similar methods were used to measure extrapyramidal symptoms (EPS) in an 8-week trial comparing 5 fixed doses of RISPERDAL® (1, 4, 8, 12, and 16 mg/day):

Dose Groups | RISPERDAL® 1 mg | RISPERDAL® 4 mg | RISPERDAL® 8 mg | RISPERDAL® 12 mg | RISPERDAL® 16 mg
Parkinsonism | 0.6 | 1.7 | 2.4 | 2.9 | 4.1
EPS Incidence | 7% | 11% | 17% | 18% | 20%

Dystonia

Class Effect: Symptoms of dystonia, prolonged abnormal contractions of muscle groups, may occur in susceptible individuals during the first few days of treatment. Dystonic symptoms include: spasm of the neck muscles, sometimes progressing to tightness of the throat, swallowing difficulty, difficulty breathing, and/or protrusion of the tongue. While these symptoms can occur at low doses, they occur more frequently and with greater severity with high potency and at higher doses of first generation antipsychotic drugs. An elevated risk of acute dystonia is observed in males and younger age groups.

Other Adverse Reactions

Adverse event data elicited by a checklist for side effects from a large study comparing 5 fixed doses of RISPERDAL® (1, 4, 8, 12, and 16 mg/day) were explored for dose-relatedness of adverse events. A Cochran-Armitage Test for trend in these data revealed a positive trend (p<0.05) for the following adverse reactions: somnolence, vision abnormal, dizziness, palpitations, weight increase, erectile dysfunction, ejaculation disorder, sexual function abnormal, fatigue, and skin discoloration.

6.7 Changes in Body Weight

The proportions of RISPERDAL® and placebo-treated adult patients with schizophrenia meeting a weight gain criterion of ≥ 7% of body weight were compared in a pool of 6- to 8-week, placebo-controlled trials, revealing a statistically significantly greater incidence of weight gain for RISPERDAL® (18%) compared to placebo (9%). In a pool of placebo-controlled 3-week studies in adult patients with acute mania, the incidence of weight increase of ≥ 7% at endpoint was comparable in the RISPERDAL® (2.5%) and placebo (2.4%) groups, and was slightly higher in the active-control group (3.5%).

Changes in body weight were also evaluated in pediatric patients [see Use in Specific Populations (8.4)]

6.8 Changes in ECG

Between-group comparisons for pooled placebo-controlled trials in adults revealed no statistically significant differences between risperidone and placebo in mean changes from baseline in ECG parameters, including QT, QTc, and PR intervals, and heart rate. When all RISPERDAL® doses were pooled from randomized controlled trials in several indications, there was a mean increase in heart rate of 1 beat per minute compared to no change for placebo patients. In short-term schizophrenia trials, higher doses of risperidone (8–16 mg/day) were associated with a higher mean increase in heart rate compared to placebo (4–6 beats per minute). In pooled placebo-controlled acute mania trials in adults, there were small decreases in mean heart rate, similar among all treatment groups.

In the two placebo-controlled trials in children and adolescents with autistic disorder (aged 5 – 16 years) mean changes in heart rate were an increase of 8.4 beats per minute in the RISPERDAL® groups and 6.5 beats per minute in the placebo group. There were no other notable ECG changes.

In a placebo-controlled acute mania trial in children and adolescents (aged 10 – 17 years), there were no significant changes in ECG parameters, other than the effect of RISPERDAL® to transiently increase pulse rate (< 6 beats per minute). In two controlled schizophrenia trials in adolescents (aged 13 – 17 years), there were no clinically meaningful changes in ECG parameters including corrected QT intervals between treatment groups or within treatment groups over time.

6.9 Postmarketing Experience

The following adverse reactions have been identified during postapproval use of risperidone; because these reactions are reported voluntarily from a population of uncertain size, it is not possible to reliably estimate their frequency: agranulocytosis, alopecia, anaphylactic reaction, angioedema, atrial fibrillation, diabetes mellitus, diabetic ketoacidosis in patients with impaired glucose metabolism, hypoglycemia, inappropriate antidiuretic hormone secretion, intestinal obstruction, jaundice, mania, pancreatitis, QT prolongation, sleep apnea, thrombocytopenia, urinary retention, and water intoxication.

Other adverse events reported since market introduction, which were temporally related to risperidone but not necessarily causally related, include the following: pituitary adenoma, pulmonary embolism, precocious puberty, cardiopulmonary arrest, and sudden death.

7 DRUG INTERACTIONS

7.1 Centrally-Acting Drugs and Alcohol

Given the primary CNS effects of risperidone, caution should be used when RISPERDAL® is taken in combination with other centrally-acting drugs and alcohol.

7.2 Drugs with Hypotensive Effects

Because of its potential for inducing hypotension, RISPERDAL® may enhance the hypotensive effects of other therapeutic agents with this potential.

7.3 Levodopa and Dopamine Agonists

RISPERDAL® may antagonize the effects of levodopa and dopamine agonists.

7.4 Amitriptyline

Amitriptyline did not affect the pharmacokinetics of risperidone or risperidone and 9-hydroxyrisperidone combined.

7.5 Cimetidine and Ranitidine

Cimetidine and ranitidine increased the bioavailability of risperidone by 64% and 26%, respectively. However, cimetidine did not affect the AUC of risperidone and 9-hydroxyrisperidone combined, whereas ranitidine increased the AUC of risperidone and 9-hydroxyrisperidone combined by 20%.

7.6 Clozapine

Chronic administration of clozapine with RISPERDAL® may decrease the clearance of risperidone.

7.7 Lithium

Repeated oral doses of RISPERDAL® (3 mg twice daily) did not affect the exposure (AUC) or peak plasma concentrations (Cmax) of lithium (n=13).

7.8 Valproate

Repeated oral doses of RISPERDAL® (4 mg once daily) did not affect the pre-dose or average plasma concentrations and exposure (AUC) of valproate (1000 mg/day in three divided doses) compared to placebo (n=21). However, there was a 20% increase in valproate peak plasma concentration (Cmax) after concomitant administration of RISPERDAL®.

7.9 Digoxin

RISPERDAL® (0.25 mg twice daily) did not show a clinically relevant effect on the pharmacokinetics of digoxin.

7.10 Drugs That Inhibit CYP 2D6 and Other CYP Isozymes

Risperidone is metabolized to 9-hydroxyrisperidone by CYP 2D6, an enzyme that is polymorphic in the population and that can be inhibited by a variety of psychotropic and other drugs [see Clinical Pharmacology (12.3)]. Drug interactions that reduce the metabolism of risperidone to 9-hydroxyrisperidone would increase the plasma concentrations of risperidone and lower the concentrations of 9-hydroxyrisperidone. Analysis of clinical studies involving a modest number of poor metabolizers (n≅70) does not suggest that poor and extensive metabolizers have different rates of adverse effects. No comparison of effectiveness in the two groups has been made.

In vitro studies showed that drugs metabolized by other CYP isozymes, including 1A1, 1A2, 2C9, 2C19, and 3A4, are only weak inhibitors of risperidone metabolism.

Fluoxetine and Paroxetine

Fluoxetine (20 mg once daily) and paroxetine (20 mg once daily) have been shown to increase the plasma concentration of risperidone 2.5–2.8 fold and 3–9 fold, respectively. Fluoxetine did not affect the plasma concentration of 9-hydroxyrisperidone. Paroxetine lowered the concentration of 9-hydroxyrisperidone by about 10%. When either concomitant fluoxetine or paroxetine is initiated or discontinued, the physician should re-evaluate the dosing of RISPERDAL®. The effects of discontinuation of concomitant fluoxetine or paroxetine therapy on the pharmacokinetics of risperidone and 9-hydroxyrisperidone have not been studied.

Erythromycin

There were no significant interactions between RISPERDAL® and erythromycin.

7.11 Carbamazepine and Other Enzyme Inducers

Carbamazepine co-administration decreased the steady-state plasma concentrations of risperidone and 9-hydroxyrisperidone by about 50%. Plasma concentrations of carbamazepine did not appear to be affected. The dose of RISPERDAL® may need to be titrated accordingly for patients receiving carbamazepine, particularly during initiation or discontinuation of carbamazepine therapy. Co-administration of other known enzyme inducers (e.g., phenytoin, rifampin, and phenobarbital) with RISPERDAL® may cause similar decreases in the combined plasma concentrations of risperidone and 9-hydroxyrisperidone, which could lead to decreased efficacy of RISPERDAL® treatment.

7.12 Drugs Metabolized by CYP 2D6

In vitro studies indicate that risperidone is a relatively weak inhibitor of CYP 2D6. Therefore, RISPERDAL® is not expected to substantially inhibit the clearance of drugs that are metabolized by this enzymatic pathway. In drug interaction studies, RISPERDAL® did not significantly affect the pharmacokinetics of donepezil and galantamine, which are metabolized by CYP 2D6.

8 USE IN SPECIFIC POPULATIONS

8.1 Pregnancy

TERATOGENIC EFFECTS

Pregnancy Category C.

The teratogenic potential of risperidone was studied in three Segment II studies in Sprague-Dawley and Wistar rats (0.63–10 mg/kg or 0.4 to 6 times the maximum recommended human dose [MRHD] on a mg/m^2 basis) and in one Segment II study in New Zealand rabbits (0.31–5 mg/kg or 0.4 to 6 times the MRHD on a mg/m^2 basis). The incidence of malformations was not increased compared to control in offspring of rats or rabbits given 0.4 to 6 times the MRHD on a mg/m^2 basis. In three reproductive studies in rats (two Segment III and a multigenerational study), there was an increase in pup deaths during the first 4 days of lactation at doses of 0.16–5 mg/kg or 0.1 to 3 times the MRHD on a mg/m^2 basis. It is not known whether these deaths were due to a direct effect on the fetuses or pups or to effects on the dams.

There was no no-effect dose for increased rat pup mortality. In one Segment III study, there was an increase in stillborn rat pups at a dose of 2.5 mg/kg or 1.5 times the MRHD on a mg/m^2 basis. In a cross-fostering study in Wistar rats, toxic effects on the fetus or pups, as evidenced by a decrease in the number of live pups and an increase in the number of dead pups at birth (Day 0), and a decrease in birth weight in pups of drug-treated dams were observed. In addition, there was an increase in deaths by Day 1 among pups of drug-treated dams, regardless of whether or not the pups were cross-fostered. Risperidone also appeared to impair maternal behavior in that pup body weight gain and survival (from Day 1 to 4 of lactation) were reduced in pups born to control but reared by drug-treated dams. These effects were all noted at the one dose of risperidone tested, i.e., 5 mg/kg or 3 times the MRHD on a mg/m^2 basis.

Placental transfer of risperidone occurs in rat pups. There are no adequate and well-controlled studies in pregnant women. However, there was one report of a case of agenesis of the corpus callosum in an infant exposed to risperidone in utero. The causal relationship to RISPERDAL® therapy is unknown. Reversible extrapyramidal symptoms in the neonate were observed following postmarketing use of RISPERDAL® during the last trimester of pregnancy.

RISPERDAL® should be used during pregnancy only if the potential benefit justifies the potential risk to the fetus.

8.2 Labor and Delivery

The effect of RISPERDAL® on labor and delivery in humans is unknown.

8.3 Nursing Mothers

In animal studies, risperidone and 9-hydroxyrisperidone are excreted in milk. Risperidone and 9-hydroxyrisperidone are also excreted in human breast milk. Therefore, women receiving RISPERDAL® should not breast-feed.

8.4 Pediatric Use

The efficacy and safety of RISPERDAL® in the treatment of schizophrenia were demonstrated in 417 adolescents, aged 13 – 17 years, in two short-term (6 and 8 weeks, respectively) double-blind controlled trials [see Indications and Usage (1.1), Adverse Reactions (6.1), and Clinical Studies (14.1)]. Additional safety and efficacy information was also assessed in one long-term (6-month) open-label extension study in 284 of these adolescent patients with schizophrenia.

Safety and effectiveness of RISPERDAL® in children less than 13 years of age with schizophrenia have not been established.

The efficacy and safety of RISPERDAL® in the short-term treatment of acute manic or mixed episodes associated with Bipolar I Disorder in 169 children and adolescent patients, aged 10 – 17 years, were demonstrated in one double-blind, placebo-controlled, 3-week trial [see Indications and Usage (1.2), Adverse Reactions (6.2), and Clinical Studies (14.2)].

Safety and effectiveness of RISPERDAL® in children less than 10 years of age with bipolar disorder have not been established.

The efficacy and safety of RISPERDAL® in the treatment of irritability associated with autistic disorder were established in two 8-week, double-blind, placebo-controlled trials in 156 children and adolescent patients, aged 5 to 16 years [see Indications and Usage (1.3), Adverse Reactions (6.3) and Clinical Studies (14.4)]. Additional safety information was also assessed in a long-term study in patients with autistic disorder, or in short- and long-term studies in more than 1200 pediatric patients with psychiatric disorders other than autistic disorder, schizophrenia, or bipolar mania who were of similar age and weight, and who received similar dosages of RISPERDAL® as patients treated for irritability associated with autistic disorder.

The safety and effectiveness of RISPERDAL® in pediatric patients less than 5 years of age with autistic disorder have not been established.

Tardive Dyskinesia

In clinical trials in 1885 children and adolescents treated with RISPERDAL®, 2 (0.1%) patients were reported to have tardive dyskinesia, which resolved on discontinuation of RISPERDAL® treatment [see also Warnings and Precautions (5.4)].

Weight Gain

In a long-term, open-label extension study in adolescent patients with schizophrenia, weight increase was reported as a treatment-emergent adverse event in 14% of patients. In 103 adolescent patients with schizophrenia, a mean increase of 9.0 kg was observed after 8 months of RISPERDAL® treatment. The majority of that increase was observed within the first 6 months. The average percentiles at baseline and 8 months, respectively, were 56 and 72 for weight, 55 and 58 for height, and 51 and 71 for body mass index.

In long-term, open-label trials (studies in patients with autistic disorder or other psychiatric disorders), a mean increase of 7.5 kg after 12 months of RISPERDAL® treatment was observed, which was higher than the expected normal weight gain (approximately 3 to 3.5 kg per year adjusted for age, based on Centers for Disease Control and Prevention normative data). The majority of that increase occurred within the first 6 months of exposure to RISPERDAL®. The average percentiles at baseline and 12 months, respectively, were 49 and 60 for weight, 48 and 53 for height, and 50 and 62 for body mass index.

In one 3-week, placebo-controlled trial in children and adolescent patients with acute manic or mixed episodes of bipolar I disorder, increases in body weight were higher in the RISPERDAL® groups than the placebo group, but not dose related (1.90 kg in the RISPERDAL® 0.5–2.5 mg group, 1.44 kg in the RISPERDAL® 3–6 mg group, and 0.65 kg in the placebo group). A similar trend was observed in the mean change from baseline in body mass index.

When treating pediatric patients with RISPERDAL® for any indication, weight gain should be assessed against that expected with normal growth. [See also Adverse Reactions (6.7)]

Somnolence

Somnolence was frequently observed in placebo-controlled clinical trials of pediatric patients with autistic disorder. Most cases were mild or moderate in severity. These events were most often of early onset with peak incidence occurring during the first two weeks of treatment, and transient with a median duration of 16 days. Somnolence was the most commonly observed adverse event in the clinical trial of bipolar disorder in children and adolescents, as well as in the schizophrenia trials in adolescents. As was seen in the autistic disorder trials, these events were most often of early onset and transient in duration. [See also Adverse Reactions (6.1, 6.2, 6.3)] Patients experiencing persistent somnolence may benefit from a change in dosing regimen [see Dosage and Administration (2.1, 2.2, 2.3)].

Hyperprolactinemia, Growth, and Sexual Maturation

RISPERDAL® has been shown to elevate prolactin levels in children and adolescents as well as in adults [see Warnings and Precautions (5.6)]. In double-blind, placebo-controlled studies of up to 8 weeks duration in children and adolescents (aged 5 to 17 years) with autistic disorder or psychiatric disorders other than autistic disorder, schizophrenia, or bipolar mania, 49% of patients who received RISPERDAL® had elevated prolactin levels compared to 2% of patients who received placebo. Similarly, in placebo-controlled trials in children and adolescents (aged 10 to 17 years) with bipolar disorder, or adolescents (aged 13 to 17 years) with schizophrenia, 82–87% of patients who received RISPERDAL® had elevated levels of prolactin compared to 3–7% of patients on placebo. Increases were dose-dependent and generally greater in females than in males across indications.

In clinical trials in 1885 children and adolescents, galactorrhea was reported in 0.8% of RISPERDAL®-treated patients and gynecomastia was reported in 2.3% of RISPERDAL®-treated patients.

The long-term effects of RISPERDAL® on growth and sexual maturation have not been fully evaluated.

8.5 Geriatric Use

Clinical studies of RISPERDAL® in the treatment of schizophrenia did not include sufficient numbers of patients aged 65 and over to determine whether or not they respond differently than younger patients. Other reported clinical experience has not identified differences in responses between elderly and younger patients. In general, a lower starting dose is recommended for an elderly patient, reflecting a decreased pharmacokinetic clearance in the elderly, as well as a greater frequency of decreased hepatic, renal, or cardiac function, and of concomitant disease or other drug therapy [see Clinical Pharmacology (12.3) and Dosage and Administration (2.4, 2.5)]. While elderly patients exhibit a greater tendency to orthostatic hypotension, its risk in the elderly may be minimized by limiting the initial dose to 0.5 mg twice daily followed by careful titration [see Warnings and Precautions (5.7)]. Monitoring of orthostatic vital signs should be considered in patients for whom this is of concern.

This drug is substantially excreted by the kidneys, and the risk of toxic reactions to this drug may be greater in patients with impaired renal function. Because elderly patients are more likely to have decreased renal function, care should be taken in dose selection, and it may be useful to monitor renal function [see Dosage and Administration (2.4)].

Concomitant use with Furosemide in Elderly Patients with Dementia-Related Psychosis

In two of four placebo-controlled trials in elderly patients with dementia-related psychosis, a higher incidence of mortality was observed in patients treated with furosemide plus RISPERDAL® when compared to patients treated with RISPERDAL® alone or with placebo plus furosemide. No pathological mechanism has been identified to explain this finding, and no consistent pattern for cause of death was observed. An increase of mortality in elderly patients with dementia-related psychosis was seen with the use of RISPERDAL® regardless of concomitant use with furosemide. RISPERDAL® is not approved for the treatment of patients with dementia-related psychosis. [See Boxed Warning and Warnings and Precautions (5.1)]

9 DRUG ABUSE AND DEPENDENCE

9.1 Controlled Substance

RISPERDAL® (risperidone) is not a controlled substance.

9.2 Abuse

RISPERDAL® has not been systematically studied in animals or humans for its potential for abuse. While the clinical trials did not reveal any tendency for any drug-seeking behavior, these observations were not systematic and it is not possible to predict on the basis of this limited experience the extent to which a CNS-active drug will be misused, diverted, and/or abused once marketed. Consequently, patients should be evaluated carefully for a history of drug abuse, and such patients should be observed closely for signs of RISPERDAL® misuse or abuse (e.g., development of tolerance, increases in dose, drug-seeking behavior).

9.3 Dependence

RISPERDAL® has not been systematically studied in animals or humans for its potential for tolerance or physical dependence.

10 OVERDOSAGE

10.1 Human Experience

Premarketing experience included eight reports of acute RISPERDAL® overdosage with estimated doses ranging from 20 to 300 mg and no fatalities. In general, reported signs and symptoms were those resulting from an exaggeration of the drug's known pharmacological effects, i.e., drowsiness and sedation, tachycardia and hypotension, and extrapyramidal symptoms. One case, involving an estimated overdose of 240 mg, was associated with hyponatremia, hypokalemia, prolonged QT, and widened QRS. Another case, involving an estimated overdose of 36 mg, was associated with a seizure.

Postmarketing experience includes reports of acute RISPERDAL® overdosage, with estimated doses of up to 360 mg. In general, the most frequently reported signs and symptoms are those resulting from an exaggeration of the drug's known pharmacological effects, i.e., drowsiness, sedation, tachycardia, hypotension, and extrapyramidal symptoms. Other adverse reactions reported since market introduction related to RISPERDAL® overdose include prolonged QT interval and convulsions. Torsade de pointes has been reported in association with combined overdose of RISPERDAL® and paroxetine.

10.2 Management of Overdosage

In case of acute overdosage, establish and maintain an airway and ensure adequate oxygenation and ventilation. Gastric lavage (after intubation, if patient is unconscious) and administration of activated charcoal together with a laxative should be considered. Because of the rapid disintegration of RISPERDAL® M-TAB®Orally Disintegrating Tablets, pill fragments may not appear in gastric contents obtained with lavage.

The possibility of obtundation, seizures, or dystonic reaction of the head and neck following overdose may create a risk of aspiration with induced emesis. Cardiovascular monitoring should commence immediately and should include continuous electrocardiographic monitoring to detect possible arrhythmias. If antiarrhythmic therapy is administered, disopyramide, procainamide, and quinidine carry a theoretical hazard of QT-prolonging effects that might be additive to those of risperidone. Similarly, it is reasonable to expect that the alpha-blocking properties of bretylium might be additive to those of risperidone, resulting in problematic hypotension.

There is no specific antidote to RISPERDAL®. Therefore, appropriate supportive measures should be instituted. The possibility of multiple drug involvement should be considered. Hypotension and circulatory collapse should be treated with appropriate measures, such as intravenous fluids and/or sympathomimetic agents (epinephrine and dopamine should not be used, since beta stimulation may worsen hypotension in the setting of risperidone-induced alpha blockade). In cases of severe extrapyramidal symptoms, anticholinergic medication should be administered. Close medical supervision and monitoring should continue until the patient recovers.

11 DESCRIPTION

RISPERDAL® contains risperidone, a psychotropic agent belonging to the chemical class of benzisoxazole derivatives. The chemical designation is 3-[2-[4-(6-fluoro-1,2-benzisoxazol-3-yl)-1-piperidinyl]ethyl]-6,7,8,9-tetrahydro-2-methyl-4H-pyrido[1,2-a]pyrimidin-4-one. Its molecular formula is C23H27FN4O2 and its molecular weight is 410.49. The structural formula is:

Risperidone is a white to slightly beige powder. It is practically insoluble in water, freely soluble in methylene chloride, and soluble in methanol and 0.1 N HCl.

RISPERDAL® Tablets are available in 0.25 mg (dark yellow), 0.5 mg (red-brown), 1 mg (white), 2 mg (orange), 3 mg (yellow), and 4 mg (green) strengths. RISPERDAL® tablets contain the following inactive ingredients: colloidal silicon dioxide, hypromellose, lactose, magnesium stearate, microcrystalline cellulose, propylene glycol, sodium lauryl sulfate, and starch (corn). The 0.25 mg, 0.5 mg, 2 mg, 3 mg, and 4 mg tablets also contain talc and titanium dioxide. The 0.25 mg tablets contain yellow iron oxide; the 0.5 mg tablets contain red iron oxide; the 2 mg tablets contain FD&C Yellow No. 6 Aluminum Lake; the 3 mg and 4 mg tablets contain D&C Yellow No. 10; the 4 mg tablets contain FD&C Blue No. 2 Aluminum Lake.

RISPERDAL® is also available as a 1 mg/mL oral solution. RISPERDAL® Oral Solution contains the following inactive ingredients: tartaric acid, benzoic acid, sodium hydroxide, and purified water.

RISPERDAL® M-TAB® Orally Disintegrating Tablets are available in 0.5 mg (light coral), 1 mg (light coral), 2 mg (coral), 3 mg (coral), and 4 mg (coral) strengths. RISPERDAL® M-TAB® Orally Disintegrating Tablets contain the following inactive ingredients: Amberlite® resin, gelatin, mannitol, glycine, simethicone, carbomer, sodium hydroxide, aspartame, red ferric oxide, and peppermint oil. In addition, the 2 mg, 3 mg, and 4 mg RISPERDAL® M-TAB® Orally Disintegrating Tablets contain xanthan gum.

12 CLINICAL PHARMACOLOGY

12.1 Mechanism of Action

The mechanism of action of RISPERDAL®, as with other drugs used to treat schizophrenia, is unknown. However, it has been proposed that the drug's therapeutic activity in schizophrenia is mediated through a combination of dopamine Type 2 (D2) and serotonin Type 2 (5HT2) receptor antagonism.

RISPERDAL® is a selective monoaminergic antagonist with high affinity (Ki of 0.12 to 7.3 nM) for the serotonin Type 2 (5HT2), dopamine Type 2 (D2), α1 and α2 adrenergic, and H1 histaminergic receptors. RISPERDAL® acts as an antagonist at other receptors, but with lower potency. RISPERDAL® has low to moderate affinity (Ki of 47 to 253 nM) for the serotonin 5HT1C, 5HT1D, and 5HT1A receptors, weak affinity (Ki of 620 to 800 nM) for the dopamine D1 and haloperidol-sensitive sigma site, and no affinity (when tested at concentrations >10^-5 M) for cholinergic muscarinic or β1 and β2 adrenergic receptors.

12.2 Pharmacodynamics

The clinical effect from RISPERDAL® results from the combined concentrations of risperidone and its major metabolite, 9-hydroxyrisperidone [see Clinical Pharmacology (12.3)]. Antagonism at receptors other than D2 and 5HT2 [see Clinical Pharmacology (12.1)] may explain some of the other effects of RISPERDAL®.

12.3 Pharmacokinetics

Absorption

Risperidone is well absorbed. The absolute oral bioavailability of risperidone is 70% (CV=25%). The relative oral bioavailability of risperidone from a tablet is 94% (CV=10%) when compared to a solution.

Pharmacokinetic studies showed that RISPERDAL® M-TAB® Orally Disintegrating Tablets and RISPERDAL® Oral Solution are bioequivalent to RISPERDAL® Tablets.

Plasma concentrations of risperidone, its major metabolite, 9-hydroxyrisperidone, and risperidone plus 9-hydroxyrisperidone are dose proportional over the dosing range of 1 to 16 mg daily (0.5 to 8 mg twice daily). Following oral administration of solution or tablet, mean peak plasma concentrations of risperidone occurred at about 1 hour. Peak concentrations of 9-hydroxyrisperidone occurred at about 3 hours in extensive metabolizers, and 17 hours in poor metabolizers. Steady-state concentrations of risperidone are reached in 1 day in extensive metabolizers and would be expected to reach steady-state in about 5 days in poor metabolizers. Steady-state concentrations of 9-hydroxyrisperidone are reached in 5–6 days (measured in extensive metabolizers).

Food Effect

Food does not affect either the rate or extent of absorption of risperidone. Thus, RISPERDAL® can be given with or without meals.

Distribution

Risperidone is rapidly distributed. The volume of distribution is 1–2 L/kg. In plasma, risperidone is bound to albumin and α1-acid glycoprotein. The plasma protein binding of risperidone is 90%, and that of its major metabolite, 9-hydroxyrisperidone, is 77%. Neither risperidone nor 9-hydroxyrisperidone displaces each other from plasma binding sites. High therapeutic concentrations of sulfamethazine (100 mcg/mL), warfarin (10 mcg/mL), and carbamazepine (10mcg/mL) caused only a slight increase in the free fraction of risperidone at 10 ng/mL and 9-hydroxyrisperidone at 50 ng/mL, changes of unknown clinical significance.

Metabolism and Drug Interactions

Risperidone is extensively metabolized in the liver. The main metabolic pathway is through hydroxylation of risperidone to 9-hydroxyrisperidone by the enzyme, CYP 2D6. A minor metabolic pathway is through N-dealkylation. The main metabolite, 9-hydroxyrisperidone, has similar pharmacological activity as risperidone. Consequently, the clinical effect of the drug results from the combined concentrations of risperidone plus 9-hydroxyrisperidone.

CYP 2D6, also called debrisoquin hydroxylase, is the enzyme responsible for metabolism of many neuroleptics, antidepressants, antiarrhythmics, and other drugs. CYP 2D6 is subject to genetic polymorphism (about 6%–8% of Caucasians, and a very low percentage of Asians, have little or no activity and are "poor metabolizers") and to inhibition by a variety of substrates and some non-substrates, notably quinidine. Extensive CYP 2D6 metabolizers convert risperidone rapidly into 9-hydroxyrisperidone, whereas poor CYP 2D6 metabolizers convert it much more slowly. Although extensive metabolizers have lower risperidone and higher 9-hydroxyrisperidone concentrations than poor metabolizers, the pharmacokinetics of risperidone and 9-hydroxyrisperidone combined, after single and multiple doses, are similar in extensive and poor metabolizers.

Risperidone could be subject to two kinds of drug-drug interactions. First, inhibitors of CYP 2D6 interfere with conversion of risperidone to 9-hydroxyrisperidone [see Drug Interactions (7.12)]. This occurs with quinidine, giving essentially all recipients a risperidone pharmacokinetic profile typical of poor metabolizers. The therapeutic benefits and adverse effects of risperidone in patients receiving quinidine have not been evaluated, but observations in a modest number (n≅70) of poor metabolizers given RISPERDAL® do not suggest important differences between poor and extensive metabolizers. Second, co-administration of known enzyme inducers (e.g., carbamazepine, phenytoin, rifampin, and phenobarbital) with RISPERDAL® may cause a decrease in the combined plasma concentrations of risperidone and 9-hydroxyrisperidone [see Drug Interactions (7.11)]. It would also be possible for risperidone to interfere with metabolism of other drugs metabolized by CYP 2D6. Relatively weak binding of risperidone to the enzyme suggests this is unlikely [see Drug Interactions 7.12)].

Excretion

Risperidone and its metabolites are eliminated via the urine and, to a much lesser extent, via the feces. As illustrated by a mass balance study of a single 1 mg oral dose of 14C-risperidone administered as solution to three healthy male volunteers, total recovery of radioactivity at 1 week was 84%, including 70% in the urine and 14% in the feces.

The apparent half-life of risperidone was 3 hours (CV=30%) in extensive metabolizers and 20 hours (CV=40%) in poor metabolizers. The apparent half-life of 9-hydroxyrisperidone was about 21 hours (CV=20%) in extensive metabolizers and 30 hours (CV=25%) in poor metabolizers. The pharmacokinetics of risperidone and 9-hydroxyrisperidone combined, after single and multiple doses, were similar in extensive and poor metabolizers, with an overall mean elimination half-life of about 20 hours.

Renal Impairment

In patients with moderate to severe renal disease, clearance of the sum of risperidone and its active metabolite decreased by 60% compared to young healthy subjects. RISPERDAL® doses should be reduced in patients with renal disease [see Dosage and Administration (2.4) and Warnings and Precautions (5.17)].

Hepatic Impairment

While the pharmacokinetics of risperidone in subjects with liver disease were comparable to those in young healthy subjects, the mean free fraction of risperidone in plasma was increased by about 35% because of the diminished concentration of both albumin and α1-acid glycoprotein. RISPERDAL® doses should be reduced in patients with liver disease [see Dosage and Administration (2.4) and Warnings and Precautions (5.17)].

Elderly

In healthy elderly subjects, renal clearance of both risperidone and 9-hydroxyrisperidone was decreased, and elimination half-lives were prolonged compared to young healthy subjects. Dosing should be modified accordingly in the elderly patients [see Dosage and Administration (2.4)].

Pediatric

The pharmacokinetics of risperidone and 9-hydroxyrisperidone in children were similar to those in adults after correcting for the difference in body weight.

Race and Gender Effects

No specific pharmacokinetic study was conducted to investigate race and gender effects, but a population pharmacokinetic analysis did not identify important differences in the disposition of risperidone due to gender (whether corrected for body weight or not) or race.

13 NONCLINICAL TOXICOLOGY

13.1 Carcinogenesis, Mutagenesis, Impairment of Fertility

Carcinogenesis

Carcinogenicity studies were conducted in Swiss albino mice and Wistar rats. Risperidone was administered in the diet at doses of 0.63 mg/kg, 2.5 mg/kg, and 10 mg/kg for 18 months to mice and for 25 months to rats. These doses are equivalent to 2.4, 9.4, and 37.5 times the maximum recommended human dose (MRHD) for schizophrenia (16 mg/day) on a mg/kg basis or 0.2, 0.75, and 3 times the MRHD (mice) or 0.4, 1.5, and 6 times the MRHD (rats) on a mg/m^2 basis. A maximum tolerated dose was not achieved in male mice. There were statistically significant increases in pituitary gland adenomas, endocrine pancreas adenomas, and mammary gland adenocarcinomas. The following table summarizes the multiples of the human dose on a mg/m^2 (mg/kg) basis at which these tumors occurred.

 |  |  | Multiples of Maximum Human Dose in mg/m^2 (mg/kg)
Tumor Type | Species | Sex | Lowest Effect Level | Highest No-Effect Level
Pituitary adenomas | mouse | female | 0.75 (9.4) | 0.2 (2.4)
Endocrine pancreas adenomas | rat | male | 1.5 (9.4) | 0.4 (2.4)
Mammary gland adenocarcinomas | mouse | female | 0.2 (2.4) | none
 | rat | female | 0.4 (2.4) | none
 | rat | male | 6.0 (37.5) | 1.5 (9.4)
Mammary gland neoplasm, Total | rat | male | 1.5 (9.4) | 0.4 (2.4)

Antipsychotic drugs have been shown to chronically elevate prolactin levels in rodents. Serum prolactin levels were not measured during the risperidone carcinogenicity studies; however, measurements during subchronic toxicity studies showed that risperidone elevated serum prolactin levels 5–6 fold in mice and rats at the same doses used in the carcinogenicity studies. An increase in mammary, pituitary, and endocrine pancreas neoplasms has been found in rodents after chronic administration of other antipsychotic drugs and is considered to be prolactin-mediated. The relevance for human risk of the findings of prolactin-mediated endocrine tumors in rodents is unknown [see Warnings and Precautions (5.6)].

Mutagenesis

No evidence of mutagenic potential for risperidone was found in the Ames reverse mutation test, mouse lymphoma assay, in vitro rat hepatocyte DNA-repair assay, in vivo micronucleus test in mice, the sex-linked recessive lethal test in Drosophila, or the chromosomal aberration test in human lymphocytes or Chinese hamster cells.

Impairment of Fertility

Risperidone (0.16 to 5 mg/kg) was shown to impair mating, but not fertility, in Wistar rats in three reproductive studies (two Segment I and a multigenerational study) at doses 0.1 to 3 times the maximum recommended human dose (MRHD) on a mg/m^2 basis. The effect appeared to be in females, since impaired mating behavior was not noted in the Segment I study in which males only were treated. In a subchronic study in Beagle dogs in which risperidone was administered at doses of 0.31 to 5 mg/kg, sperm motility and concentration were decreased at doses 0.6 to 10 times the MRHD on a mg/m^2 basis. Dose-related decreases were also noted in serum testosterone at the same doses. Serum testosterone and sperm parameters partially recovered, but remained decreased after treatment was discontinued. No no-effect doses were noted in either rat or dog.

14 CLINICAL STUDIES

14.1 Schizophrenia

Adults

Short-Term Efficacy

The efficacy of RISPERDAL® in the treatment of schizophrenia was established in four short-term (4- to 8-week) controlled trials of psychotic inpatients who met DSM-III-R criteria for schizophrenia.

Several instruments were used for assessing psychiatric signs and symptoms in these studies, among them the Brief Psychiatric Rating Scale (BPRS), a multi-item inventory of general psychopathology traditionally used to evaluate the effects of drug treatment in schizophrenia. The BPRS psychosis cluster (conceptual disorganization, hallucinatory behavior, suspiciousness, and unusual thought content) is considered a particularly useful subset for assessing actively psychotic schizophrenic patients. A second traditional assessment, the Clinical Global Impression (CGI), reflects the impression of a skilled observer, fully familiar with the manifestations of schizophrenia, about the overall clinical state of the patient. In addition, the Positive and Negative Syndrome Scale (PANSS) and the Scale for Assessing Negative Symptoms (SANS) were employed.

The results of the trials follow:

- (1)In a 6-week, placebo-controlled trial (n=160) involving titration of RISPERDAL® in doses up to 10 mg/day (twice-daily schedule), RISPERDAL® was generally superior to placebo on the BPRS total score, on the BPRS psychosis cluster, and marginally superior to placebo on the SANS.
- (2)In an 8-week, placebo-controlled trial (n=513) involving 4 fixed doses of RISPERDAL® (2 mg/day, 6 mg/day, 10 mg/day, and 16 mg/day, on a twice-daily schedule), all 4 RISPERDAL® groups were generally superior to placebo on the BPRS total score, BPRS psychosis cluster, and CGI severity score; the 3 highest RISPERDAL® dose groups were generally superior to placebo on the PANSS negative subscale. The most consistently positive responses on all measures were seen for the 6 mg dose group, and there was no suggestion of increased benefit from larger doses.
- (3)In an 8-week, dose comparison trial (n=1356) involving 5 fixed doses of RISPERDAL® (1 mg/day, 4 mg/day, 8 mg/day, 12 mg/day, and 16 mg/day, on a twice-daily schedule), the four highest RISPERDAL® dose groups were generally superior to the 1 mg RISPERDAL® dose group on BPRS total score, BPRS psychosis cluster, and CGI severity score. None of the dose groups were superior to the 1 mg group on the PANSS negative subscale. The most consistently positive responses were seen for the 4 mg dose group.
- (4)In a 4-week, placebo-controlled dose comparison trial (n=246) involving 2 fixed doses of RISPERDAL® (4 and 8 mg/day on a once-daily schedule), both RISPERDAL® dose groups were generally superior to placebo on several PANSS measures, including a response measure (>20% reduction in PANSS total score), PANSS total score, and the BPRS psychosis cluster (derived from PANSS). The results were generally stronger for the 8 mg than for the 4 mg dose group.

Long-Term Efficacy

In a longer-term trial, 365 adult outpatients predominantly meeting DSM-IV criteria for schizophrenia and who had been clinically stable for at least 4 weeks on an antipsychotic medication were randomized to RISPERDAL® (2–8 mg/day) or to an active comparator, for 1 to 2 years of observation for relapse. Patients receiving RISPERDAL® experienced a significantly longer time to relapse over this time period compared to those receiving the active comparator.

Pediatrics

The efficacy of RISPERDAL® in the treatment of schizophrenia in adolescents aged 13–17 years was demonstrated in two short-term (6 and 8 weeks), double-blind controlled trials. All patients met DSM-IV diagnostic criteria for schizophrenia and were experiencing an acute episode at time of enrollment. In the first trial (study #1), patients were randomized into one of three treatment groups: RISPERDAL® 1–3 mg/day (n = 55, mean modal dose = 2.6 mg), RISPERDAL® 4–6 mg/day (n = 51, mean modal dose = 5.3 mg), or placebo (n = 54). In the second trial (study #2), patients were randomized to either RISPERDAL® 0.15–0.6 mg/day (n = 132, mean modal dose = 0.5 mg) or RISPERDAL® 1.5–6 mg/day (n = 125, mean modal dose = 4 mg). In all cases, study medication was initiated at 0.5 mg/day (with the exception of the 0.15–0.6 mg/day group in study #2, where the initial dose was 0.05 mg/day) and titrated to the target dosage range by approximately Day 7. Subsequently, dosage was increased to the maximum tolerated dose within the target dose range by Day 14. The primary efficacy variable in all studies was the mean change from baseline in total PANSS score.

Results of the studies demonstrated efficacy of RISPERDAL® in all dose groups from 1–6 mg/day compared to placebo, as measured by significant reduction of total PANSS score. The efficacy on the primary parameter in the 1–3 mg/day group was comparable to the 4–6 mg/day group in study #1, and similar to the efficacy demonstrated in the 1.5–6 mg/day group in study #2. In study #2, the efficacy in the 1.5–6 mg/day group was statistically significantly greater than that in the 0.15–0.6 mg/day group. Doses higher than 3 mg/day did not reveal any trend towards greater efficacy.

14.2 Bipolar Mania - Monotherapy

Adults

The efficacy of RISPERDAL® in the treatment of acute manic or mixed episodes was established in two short-term (3-week) placebo-controlled trials in patients who met the DSM-IV criteria for Bipolar I Disorder with manic or mixed episodes. These trials included patients with or without psychotic features.

The primary rating instrument used for assessing manic symptoms in these trials was the Young Mania Rating Scale (YMRS), an 11-item clinician-rated scale traditionally used to assess the degree of manic symptomatology (irritability, disruptive/aggressive behavior, sleep, elevated mood, speech, increased activity, sexual interest, language/thought disorder, thought content, appearance, and insight) in a range from 0 (no manic features) to 60 (maximum score). The primary outcome in these trials was change from baseline in the YMRS total score. The results of the trials follow:

- (1)In one 3-week placebo-controlled trial (n=246), limited to patients with manic episodes, which involved a dose range of RISPERDAL® 1–6 mg/day, once daily, starting at 3 mg/day (mean modal dose was 4.1 mg/day), RISPERDAL® was superior to placebo in the reduction of YMRS total score.
- (2)In another 3-week placebo-controlled trial (n=286), which involved a dose range of 1–6 mg/day, once daily, starting at 3 mg/day (mean modal dose was 5.6 mg/day), RISPERDAL® was superior to placebo in the reduction of YMRS total score.

Pediatrics

The efficacy of RISPERDAL® in the treatment of mania in children or adolescents with Bipolar I disorder was demonstrated in a 3-week, randomized, double-blind, placebo-controlled, multicenter trial including patients ranging in ages from 10 to 17 years who were experiencing a manic or mixed episode of bipolar I disorder. Patients were randomized into one of three treatment groups: RISPERDAL® 0.5–2.5 mg/day (n = 50, mean modal dose = 1.9 mg), RISPERDAL® 3–6 mg/day (n = 61, mean modal dose = 4.7 mg), or placebo (n = 58). In all cases, study medication was initiated at 0.5 mg/day and titrated to the target dosage range by Day 7, with further increases in dosage to the maximum tolerated dose within the targeted dose range by Day 10. The primary rating instrument used for assessing efficacy in this study was the mean change from baseline in the total YMRS score.

Results of this study demonstrated efficacy of RISPERDAL® in both dose groups compared with placebo, as measured by significant reduction of total YMRS score. The efficacy on the primary parameter in the 3–6 mg/day dose group was comparable to the 0.5–2.5 mg/day dose group. Doses higher than 2.5 mg/day did not reveal any trend towards greater efficacy.

14.3 Bipolar Mania – Combination Therapy

The efficacy of RISPERDAL® with concomitant lithium or valproate in the treatment of acute manic or mixed episodes was established in one controlled trial in adult patients who met the DSM-IV criteria for Bipolar I Disorder. This trial included patients with or without psychotic features and with or without a rapid-cycling course.

- (1)In this 3-week placebo-controlled combination trial, 148 in- or outpatients on lithium or valproate therapy with inadequately controlled manic or mixed symptoms were randomized to receive RISPERDAL®, placebo, or an active comparator, in combination with their original therapy. RISPERDAL®, in a dose range of 1–6 mg/day, once daily, starting at 2 mg/day (mean modal dose of 3.8 mg/day), combined with lithium or valproate (in a therapeutic range of 0.6 mEq/L to 1.4 mEq/L or 50 mcg/mL to 120 mcg/mL, respectively) was superior to lithium or valproate alone in the reduction of YMRS total score.
- (2)In a second 3-week placebo-controlled combination trial, 142 in- or outpatients on lithium, valproate, or carbamazepine therapy with inadequately controlled manic or mixed symptoms were randomized to receive RISPERDAL® or placebo, in combination with their original therapy. RISPERDAL®, in a dose range of 1–6 mg/day, once daily, starting at 2 mg/day (mean modal dose of 3.7 mg/day), combined with lithium, valproate, or carbamazepine (in therapeutic ranges of 0.6 mEq/L to 1.4 mEq/L for lithium, 50 mcg/mL to 125 mcg/mL for valproate, or 4–12 mcg/mL for carbamazepine, respectively) was not superior to lithium, valproate, or carbamazepine alone in the reduction of YMRS total score. A possible explanation for the failure of this trial was induction of risperidone and 9-hydroxyrisperidone clearance by carbamazepine, leading to subtherapeutic levels of risperidone and 9-hydroxyrisperidone.

14.4 Irritability Associated with Autistic Disorder

Short-Term Efficacy

The efficacy of RISPERDAL® in the treatment of irritability associated with autistic disorder was established in two 8-week, placebo-controlled trials in children and adolescents (aged 5 to 16 years) who met the DSM-IV criteria for autistic disorder. Over 90% of these subjects were under 12 years of age and most weighed over 20 kg (16–104.3 kg).

Efficacy was evaluated using two assessment scales: the Aberrant Behavior Checklist (ABC) and the Clinical Global Impression - Change (CGI-C) scale. The primary outcome measure in both trials was the change from baseline to endpoint in the Irritability subscale of the ABC (ABC-I). The ABC-I subscale measured the emotional and behavioral symptoms of autism, including aggression towards others, deliberate self-injuriousness, temper tantrums, and quickly changing moods. The CGI-C rating at endpoint was a co-primary outcome measure in one of the studies.

The results of these trials are as follows:

- (1)In one of the 8-week, placebo-controlled trials, children and adolescents with autistic disorder (n=101), aged 5 to 16 years, received twice daily doses of placebo or RISPERDAL® 0.5–3.5 mg/day on a weight-adjusted basis. RISPERDAL®, starting at 0.25 mg/day or 0.5 mg/day depending on baseline weight (< 20 kg and ≥ 20 kg, respectively) and titrated to clinical response (mean modal dose of 1.9 mg/day, equivalent to 0.06 mg/kg/day), significantly improved scores on the ABC-I subscale and on the CGI-C scale compared with placebo.
- (2)In the other 8-week, placebo-controlled trial in children with autistic disorder (n=55), aged 5 to 12 years, RISPERDAL® 0.02 to 0.06 mg/kg/day given once or twice daily, starting at 0.01 mg/kg/day and titrated to clinical response (mean modal dose of 0.05 mg/kg/day, equivalent to 1.4 mg/day), significantly improved scores on the ABC-I subscale compared with placebo.

Long-Term Efficacy

Following completion of the first 8-week double-blind study, 63 patients entered an open-label study extension where they were treated with RISPERDAL® for 4 or 6 months (depending on whether they received RISPERDAL® or placebo in the double-blind study). During this open-label treatment period, patients were maintained on a mean modal dose of RISPERDAL® of 1.8–2.1 mg/day (equivalent to 0.05 – 0.07 mg/kg/day).

Patients who maintained their positive response to RISPERDAL® (response was defined as ≥ 25% improvement on the ABC-I subscale and a CGI-C rating of 'much improved' or 'very much improved') during the 4–6 month open-label treatment phase for about 140 days, on average, were randomized to receive RISPERDAL® or placebo during an 8-week, double-blind withdrawal study (n=39 of the 63 patients). A pre-planned interim analysis of data from patients who completed the withdrawal study (n=32), undertaken by an independent Data Safety Monitoring Board, demonstrated a significantly lower relapse rate in the RISPERDAL® group compared with the placebo group. Based on the interim analysis results, the study was terminated due to demonstration of a statistically significant effect on relapse prevention. Relapse was defined as ≥ 25% worsening on the most recent assessment of the ABC-I subscale (in relation to baseline of the randomized withdrawal phase).

16 HOW SUPPLIED/STORAGE AND HANDLING

RISPERDAL® (risperidone) Tablets

RISPERDAL® (risperidone) Tablets are imprinted "JANSSEN" on one side and either "R1", or "R3" according to their respective strengths.

1 mg white, capsule-shaped tablets: bottles of 15 NDC 21695-113-15

3 mg yellow, capsule-shaped tablets: bottles of 30 NDC 21695-115-30 and bottles of 60 NDC 21695-113-60.

Storage and Handling

RISPERDAL® Tablets should be stored at controlled room temperature 15°–25°C (59°–77°F). Protect from light and moisture.

Keep out of reach of children.

17 PATIENT COUNSELING INFORMATION

Physicians are advised to discuss the following issues with patients for whom they prescribe RISPERDAL®:

17.1 Orthostatic Hypotension

Patients should be advised of the risk of orthostatic hypotension, especially during the period of initial dose titration [see Warnings and Precautions (5.7)].

17.2 Interference with Cognitive and Motor Performance

Since RISPERDAL® has the potential to impair judgment, thinking, or motor skills, patients should be cautioned about operating hazardous machinery, including automobiles, until they are reasonably certain that RISPERDAL® therapy does not affect them adversely [see Warnings and Precautions (5.9)].

17.3 Pregnancy

Patients should be advised to notify their physician if they become pregnant or intend to become pregnant during therapy [see Use in Specific Populations (8.1)].

17.4 Nursing

Patients should be advised not to breast-feed an infant if they are taking RISPERDAL® [see Use in Specific Populations (8.3)].

17.5 Concomitant Medication

Patients should be advised to inform their physicians if they are taking, or plan to take, any prescription or over-the-counter drugs, since there is a potential for interactions [see Drug Interactions (7)].

17.6 Alcohol

Patients should be advised to avoid alcohol while taking RISPERDAL® [see Drug Interactions (7.1)].

17.7 Phenylketonurics

Phenylalanine is a component of aspartame. Each 4 mg RISPERDAL® M-TAB® Orally Orally Disintegrating Tablet contains 0.14 mg phenylalanine.

Revised April 2010
© Ortho-McNeil-Janssen Pharmaceuticals, Inc. 2007

RISPERDAL® Tablets are manufactured by:
Janssen Ortho LLC, Gurabo, Puerto Rico 00778
RISPERDAL® Oral Solution is manufactured by:
Janssen Pharmaceutica N.V.
Beerse, Belgium

MEDICATION GUIDE

DOSAGE: For information about the use of RISPERDAL® (risperidone), please see accompanying Package Insert.

STORAGE: Store bottle at controlled room temperature (59°-77°F/15°–25°C) away from children; avoid freezing and protect from light.

Manufactured by:
Janssen Pharmaceutica N.V.
Beerse, Belgium

Manufactured for:
Janssen, Division of Ortho-McNeil-Janssen
Pharmaceuticals, Inc.
Titusville, NJ, United States 08560

MEDICATION GUIDE

Posologia: Para información acerca del uso de RISPERDAL® (risperidona), sirvase leer el prospecto adjunto en el paquete.

Almacenamiento: Almacene el frasco a temperatura ambiente controlada (59°-77°F/15° -25°C) lejos de los niños; evite que se congele y protéjalo de la luz.

Manufacturado por:
Janssen Pharmaceutica N.V.
Beerse, Bélgica

Manufacturado para:
Janssen, Division of Ortho-McNeil-Janssen
Pharmaceuticals, Inc.
Titusville, NJ, Estados Unidos 08560

Repackaged by:

Rebel Distributors Corp

Thousand Oaks, CA 91320

pRINCIPLE DISPLAY PANEL

Phenylketonurics: Contains 0.14 mg
phenylalanine (a component of aspartame)
per 0.5 mg tablet.

Dosage: For information or use, see accompanying full Prescribing Information.

Store at controlled room temperature
15°C–25°C (59°F–77°F).

Protect from light and moisture.

Keep out of reach of children.

Janssen Pharmaceutica Products, L.P.
Titusville, NJ 08560
U.S. Patent No. 4,804,663